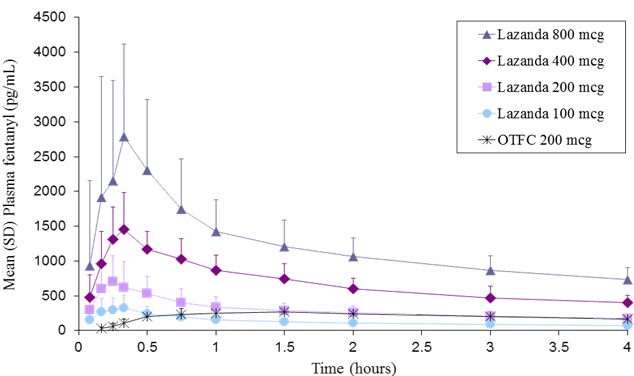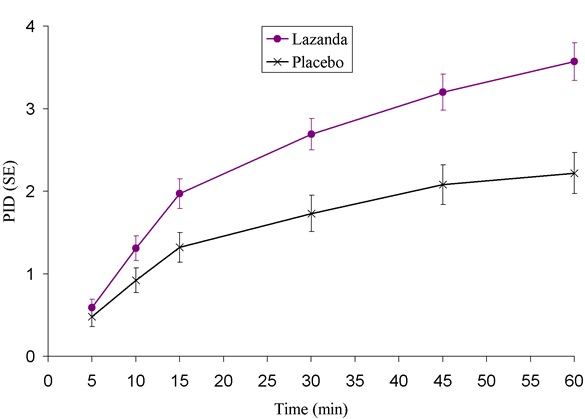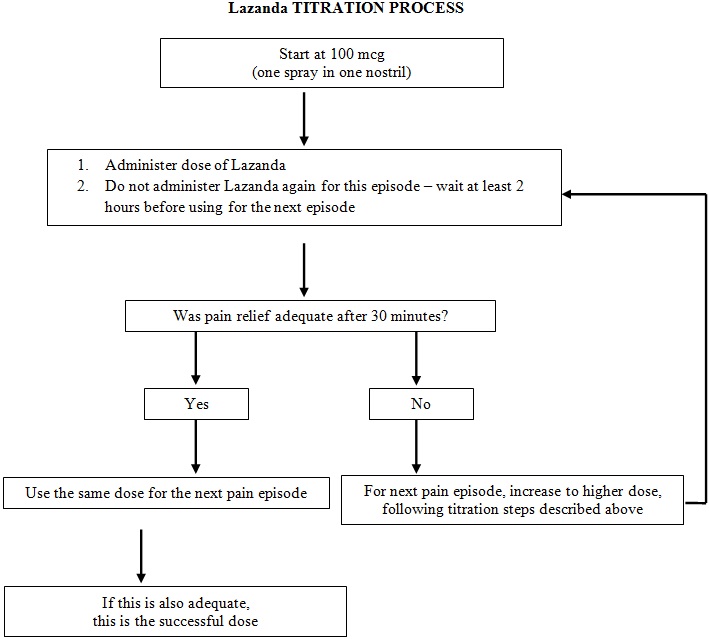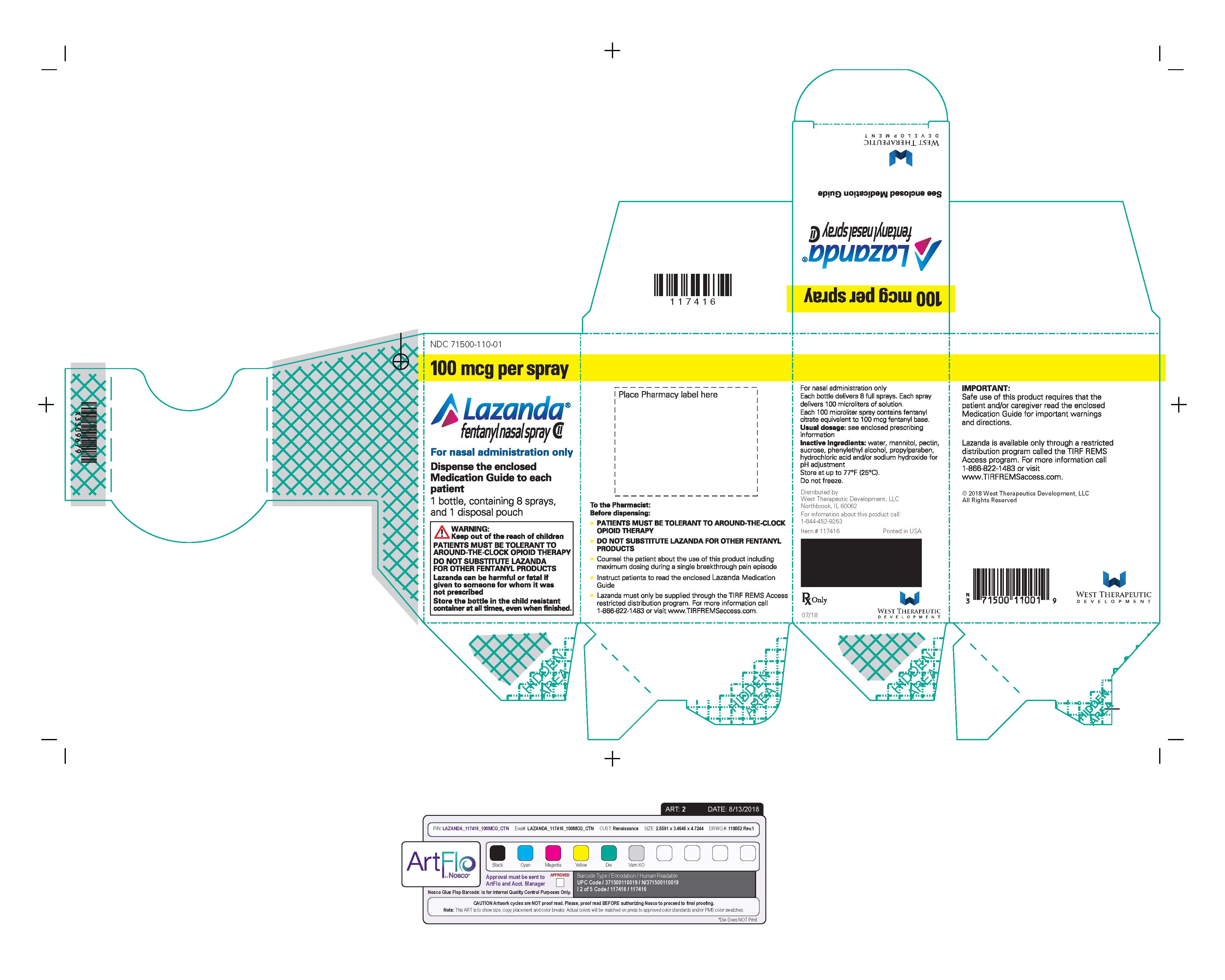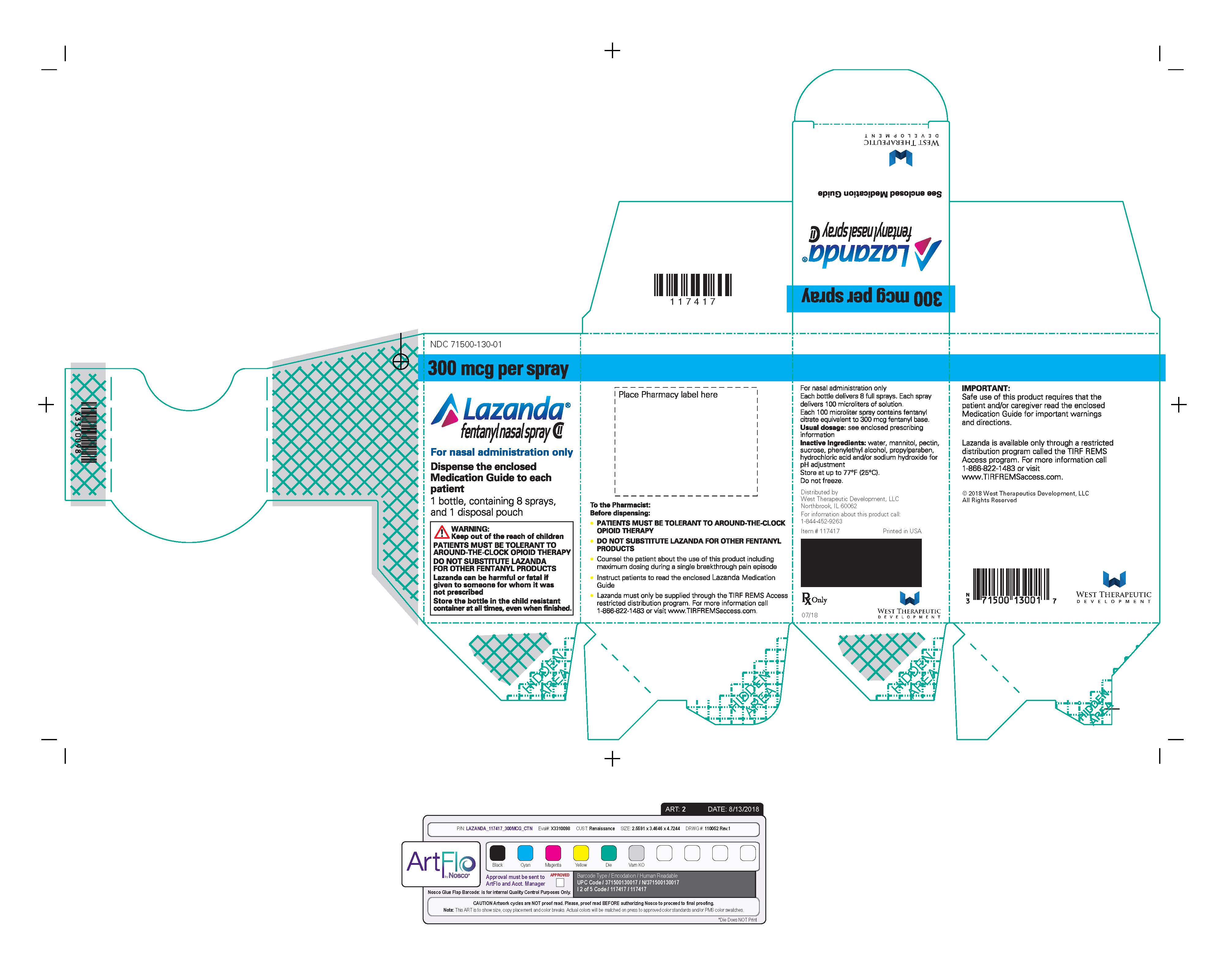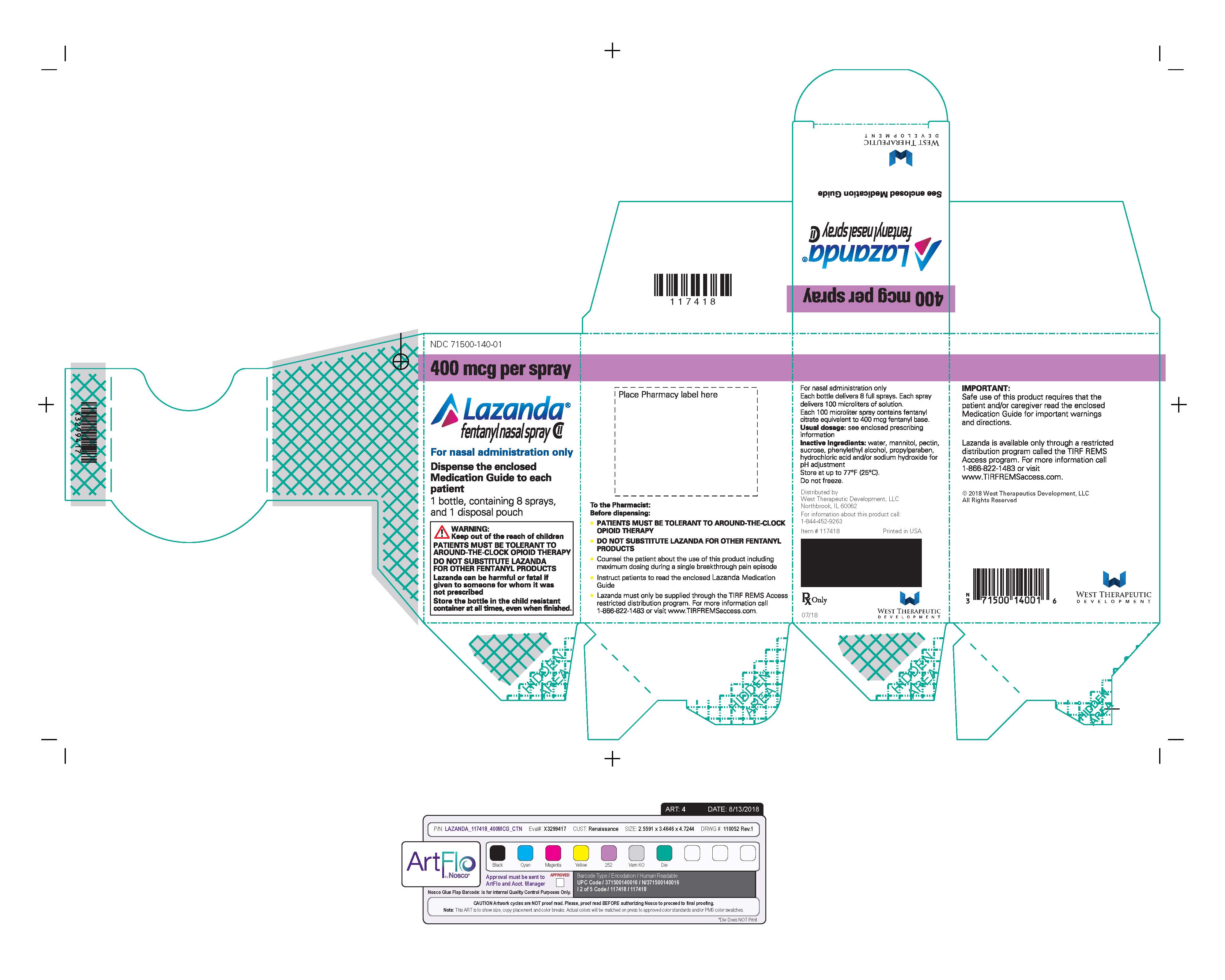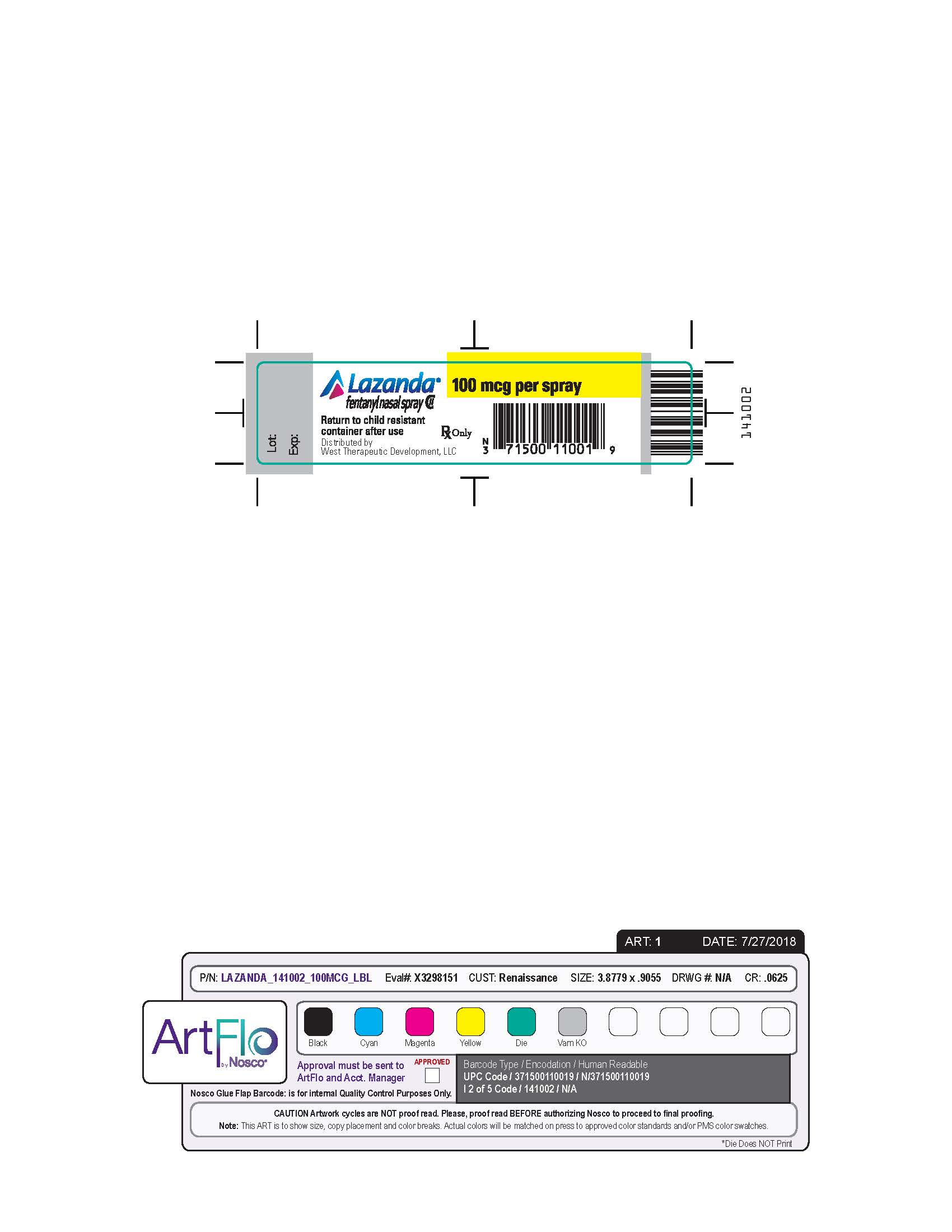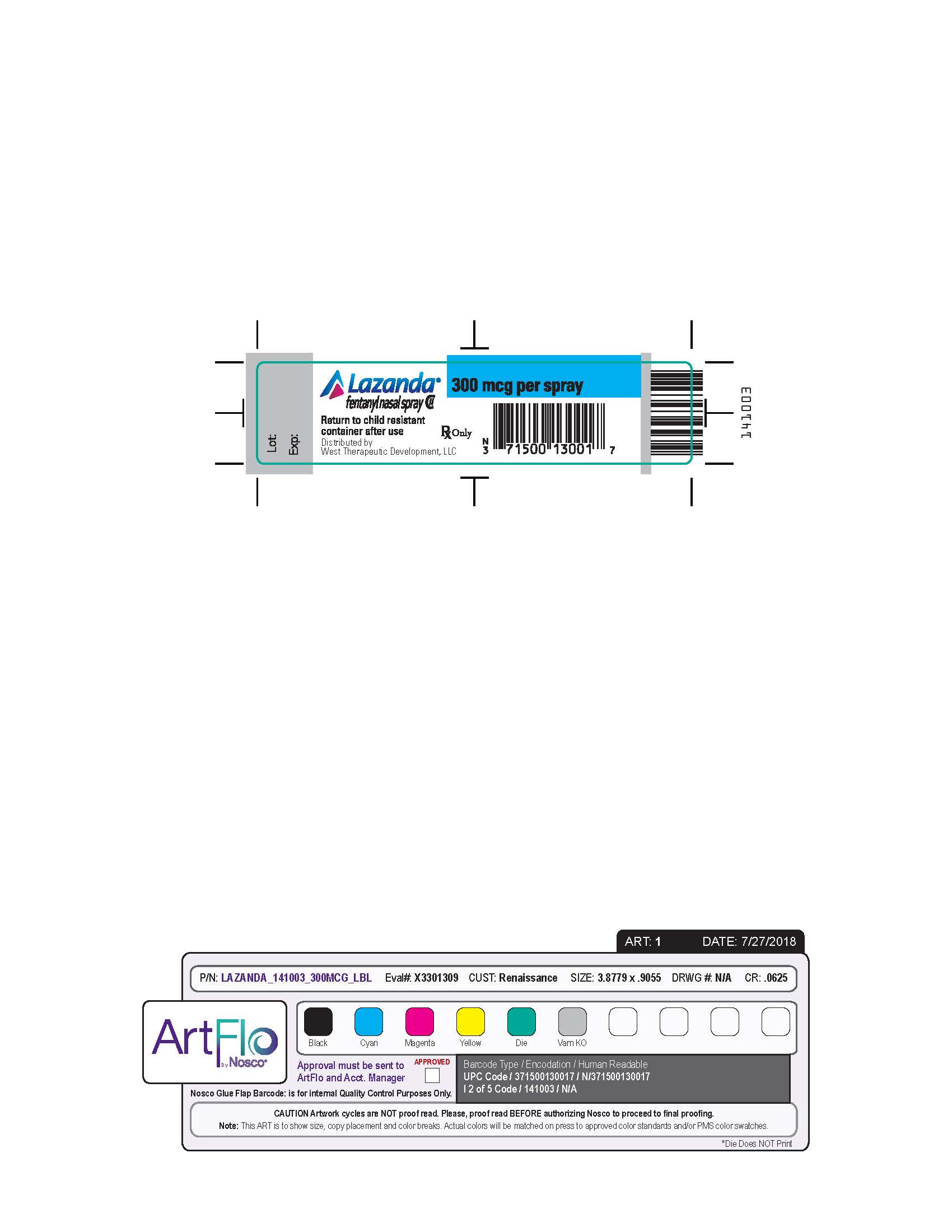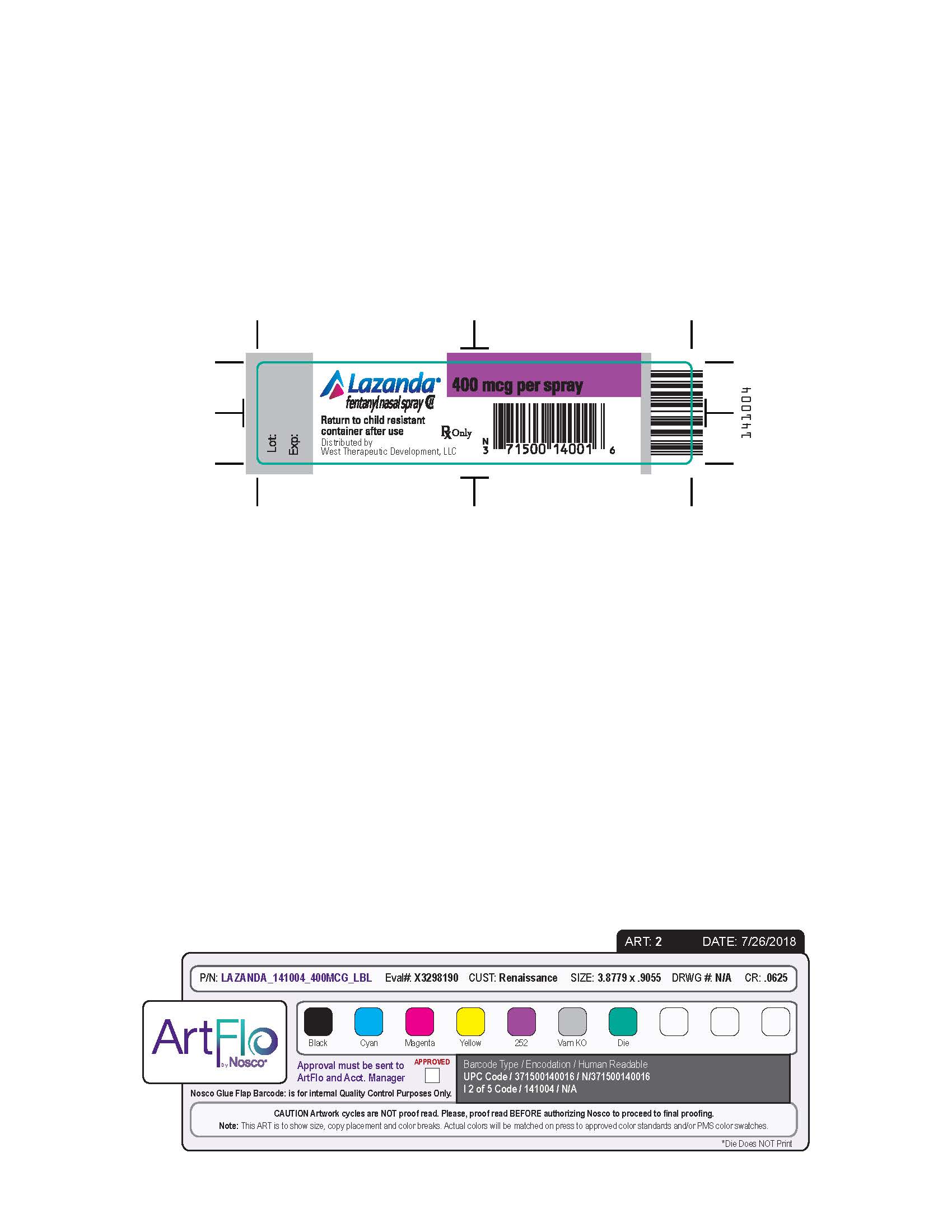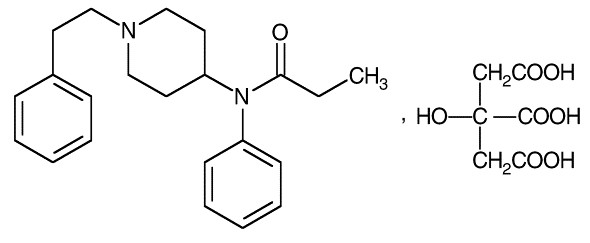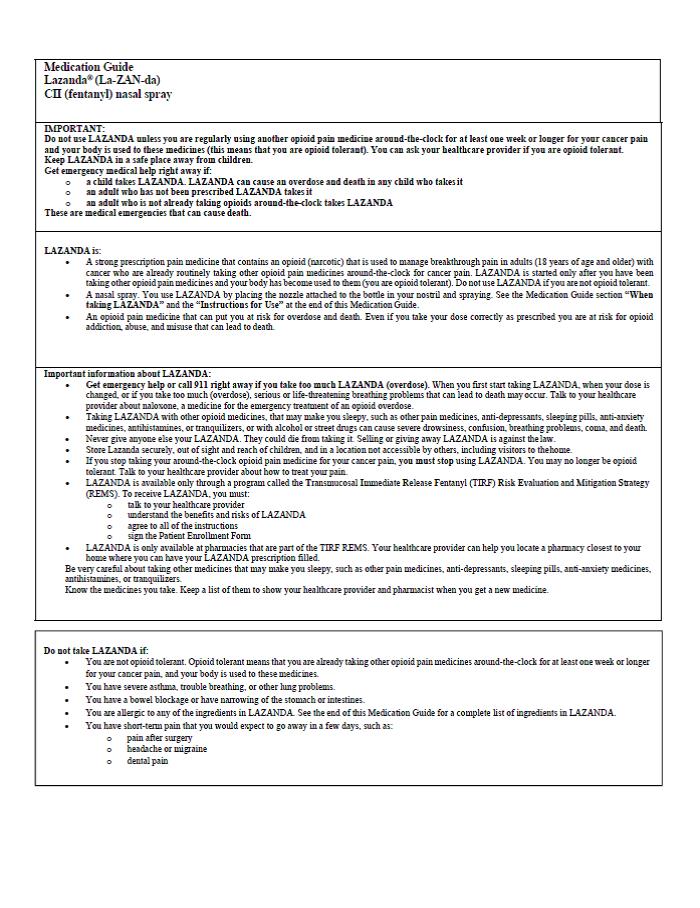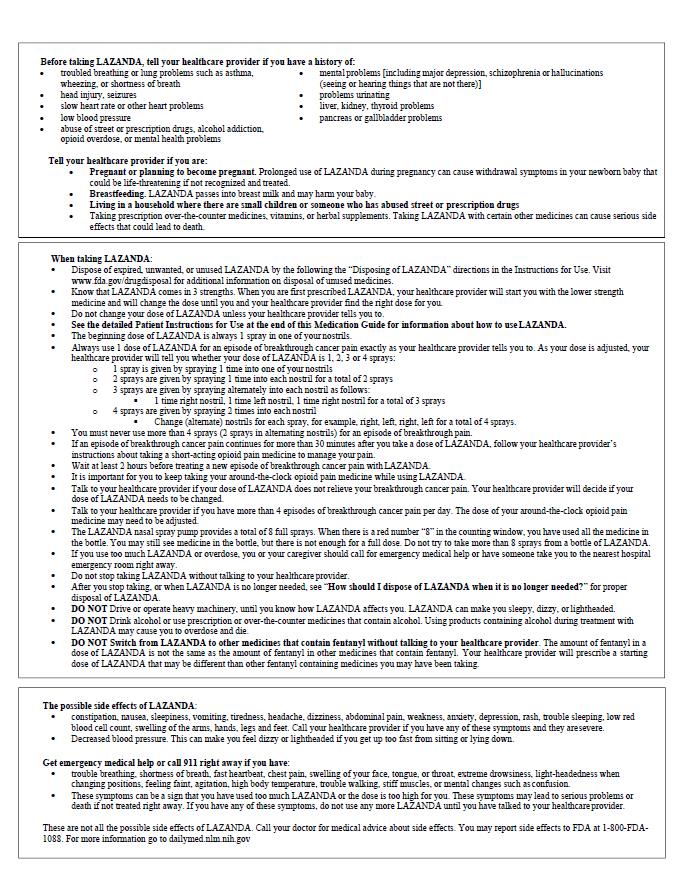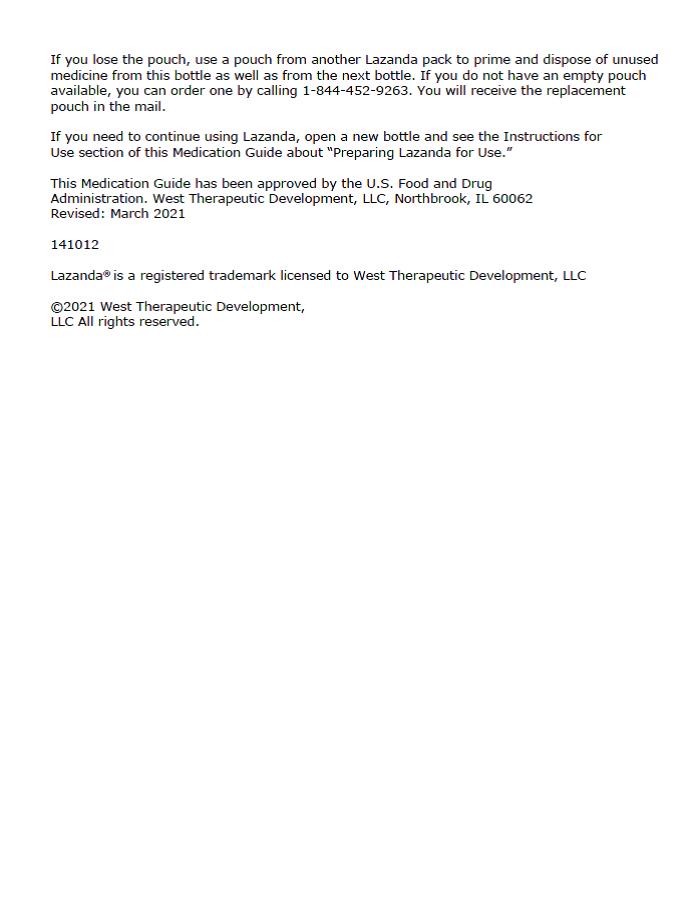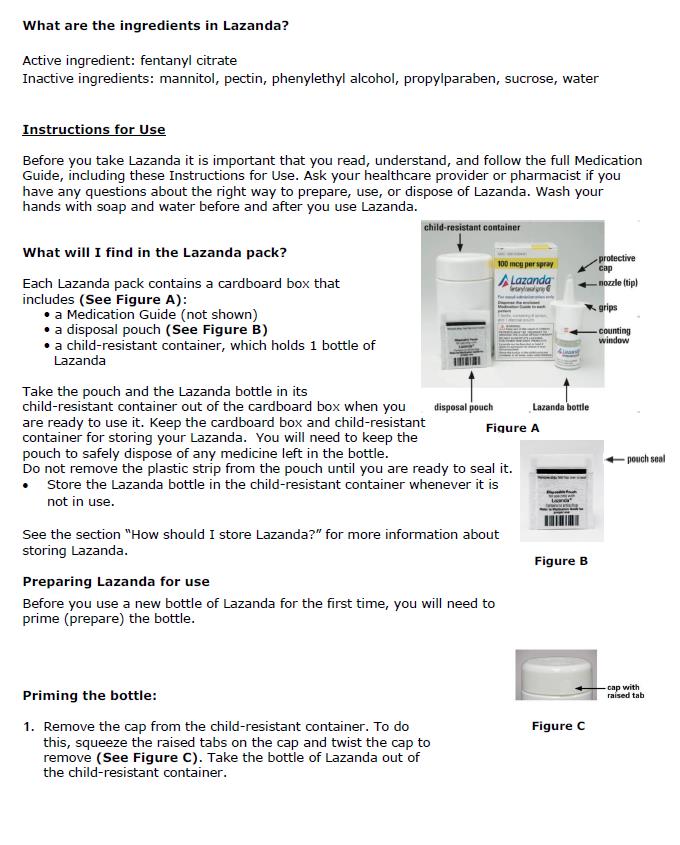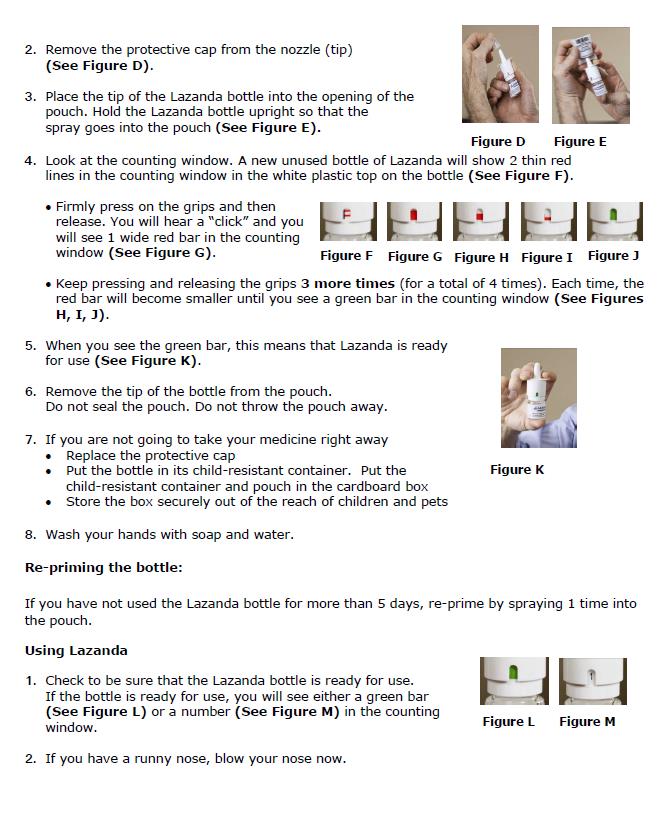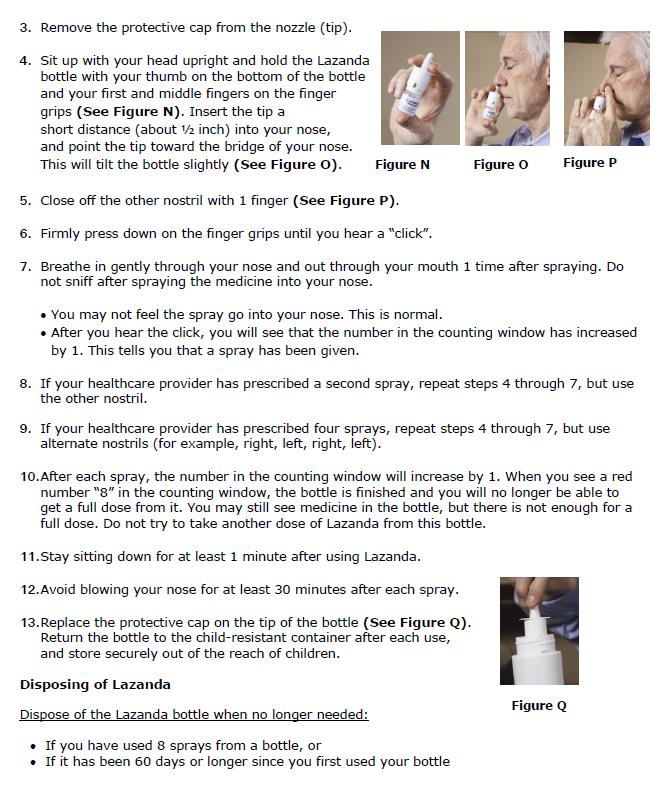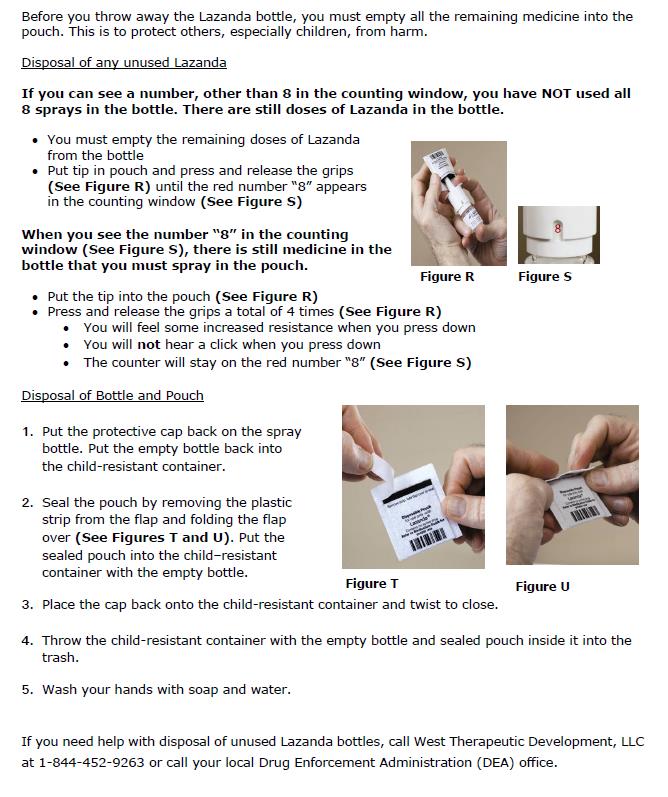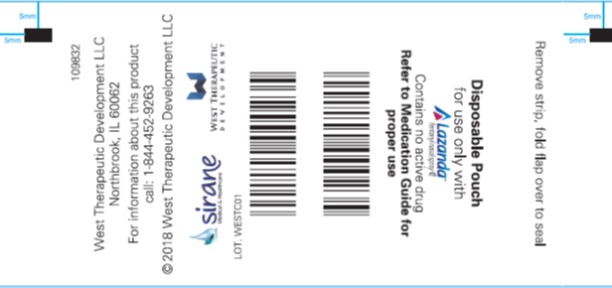 DRUG LABEL: LAZANDA
NDC: 71500-140 | Form: SPRAY
Manufacturer: West Therapeutic Development LLC
Category: prescription | Type: HUMAN PRESCRIPTION DRUG LABEL
Date: 20210331
DEA Schedule: CII

ACTIVE INGREDIENTS: FENTANYL CITRATE 400 ug/1 1
INACTIVE INGREDIENTS: COPOVIDONE K25-31; CELLULOSE, MICROCRYSTALLINE; WATER; PHENYLETHYL ALCOHOL; PECTIN; HYPROMELLOSES; MAGNESIUM STEARATE; MANNITOL; SUCROSE; PROPYLPARABEN

Lazanda (fentanyl citrate) Nasal Spray, 100 mcg, 300 mcg, 400 mcg

BOXED WARNING

WARNING: LIFE-THREATENING RESPIRATORY DEPRESSION; ACCIDENTAL EXPOSURE; CYTOCHROME P450 3A4 INTERACTION; CONCOMITANT USE WITH BENZODIAZEPINES OR OTHER CNS DEPRESSANTS; RISK OF MEDICATION ERRORS; ADDICTION, ABUSE, AND MISUSE; REMS; and NEONATAL OPIOID WITHDRAWAL SYNDROME

Life-Threatening Respiratory Depression

Serious, life-threatening, and/or fatal respiratory depression has occurred in patients treated with LAZANDA, including following use in opioid non-tolerant patients and improper dosing. Monitor for respiratory depression, especially during initiation of LAZANDA or following a dose increase. The substitution of LAZANDA for any other fentanyl product may result in fatal overdose [see Warnings and Precautions (5.1)].

Due to the risk of respiratory depression, LAZANDA is contraindicated in the management of acute or postoperative pain including headache/migraine and in opioid non-tolerant patients. [see Contraindications (4)]

Accidental Exposure

Accidental exposure of even one dose of LAZANDA, especially in children, can result in a fatal overdose of fentanyl [see Warnings and Precautions (5.1)]. Death has been reported in children who have accidentally ingested transmucosal immediate-release fentanyl products. LAZANDA must be kept out of reach of children [see Warnings and Precautions (5.2)].

Cytochrome P450 3A4 Interaction

The concomitant use of LAZANDA with all cytochrome P450 3A4 inhibitors may result in an increase in fentanyl plasma concentrations, which could increase or prolong adverse reactions and may cause potentially fatal respiratory depression. In addition, discontinuation of a concomitantly used cytochrome P450 3A4 inducer may result in an increase in fentanyl plasma concentration. Monitor patients receiving LAZANDA and any CYP3A4 inhibitor or inducer [see Warnings and Precautions (5.3), Drug Interactions (7), Clinical Pharmacology (12.2)].

Risks from Concomitant Use with Benzodiazepines or Other CNS Depressants

Concomitant use of opioids with benzodiazepines or other central nervous system (CNS) depressants, including alcohol, may result in profound sedation, respiratory depression, coma, and death [see Warnings and Precautions (5.4), Drug Interactions (7)].

- Reserve concomitant prescribing of LAZANDA and benzodiazepines or other CNS depressants for use in patients for whom alternative treatment options are inadequate.
- Limit dosages and durations to the minimum required.
- Follow patients for signs and symptoms of respiratory depression and sedation.

Risk of Medication Errors

Substantial differences exist in the pharmacokinetic profile of LAZANDA compared to other fentanyl products that result in clinically important differences in the extent of absorption of fentanyl that could result in fatal overdose [see Dosage and Administration (2.1), Warnings and Precautions (5.5)].

- When prescribing, do not convert patients on a mcg per mcg basis from any other fentanyl products to LAZANDA.
- When dispensing, do not substitute a LAZANDA prescription for other fentanyl products.

Addiction, Abuse, and Misuse

LAZANDA exposes patients and other users to the risks of opioid addiction, abuse, and misuse, which can lead to overdose and death. Assess each patient’s risk prior to prescribing LAZANDA, and monitor all patients regularly for the development of these behaviors and conditions [see Warnings and Precautions (5.6)].

Risk Evaluation and Mitigation Strategy (REMS) Access Program

Because of the risk for accidental exposure, misuse, abuse, addiction, and overdose, LAZANDA is available only through a restricted program required by the Food and Drug Administration, called a Risk Evaluation and Mitigation Strategy (REMS). Under the Transmucosal Immediate Release Fentanyl (TIRF) REMS, pharmacies, outpatients, and healthcare professionals who prescribe to outpatients must enroll in the program. Inpatient pharmacies must develop policies and procedures to verify opioid tolerance in inpatients who require LAZANDA while hospitalized [see Warnings and Precautions (5.7)] Further information is available at www.TIRFREMSaccess.com or by calling 1-866-822-1483.

Neonatal Opioid Withdrawal Syndrome

Prolonged use of LAZANDA during pregnancy can result in neonatal opioid withdrawal syndrome, which may be life-threatening if not recognized and treated, and requires management according to protocols developed by neonatology experts. If opioid use is required for a prolonged period in a pregnant woman, advise the patient of the risk of neonatal opioid withdrawal syndrome and ensure that appropriate treatment will be available [see Warnings and Precautions (5.8)]

HIGHLIGHTS OF PRESCRIBING INFORMATION

These highlights do not include all the information needed to use LAZANDA safely and effectively. See full prescribing information for LAZANDA

LAZANDA® (Fentanyl) Nasal Spray CII

Initial U.S. Approval: 1968

WARNING: LIFE-THREATENING RESPIRATORY DEPRESSION; ACCIDENTAL EXPOSURE; CYTOCHROME P450 3A4 INTERACTION; RISKS FROM CONCOMITANT USE WITH BENZODIAZEPINES OR OTHER CNS DEPRESSANTS; RISK OF MEDICATION ERRORS; ADDICTION, ABUSE, AND MISUSE; REMS; and NEONATAL OPIOID WITHDRAWAL SYNDROME

See full prescribing information for complete boxed warning.

- Serious, life-threatening, and/or fatal respiratory depression has occurred. Monitor closely, especially upon initiation or following a dose increase. Due to the risk of fatal respiratory depression, LAZANDA is contraindicated in opioid non-tolerant patients and in management of acute or postoperative pain, including headache/migraines. (4, 5.1)
- Accidental exposure of LAZANDA, especially in children, can result in a fatal overdose of fentanyl. Keep out of reach of Children. Ensure proper storage and disposal. (5.2)
- Concomitant use with CYP3A4 inhibitors (or discontinuation of CYP3A4 inducers) can result in a fatal overdose of fentanyl. (5.3, 7)
- Concomitant use of opioids with benzodiazepines or other central nervous system (CNS) depressants, including alcohol, may result in profound sedation, respiratory depression, coma, and death. Reserve concomitant prescribing for use in patients for whom alternative treatment options are inadequate; limit dosages and durations to the minimum required and follow patients for signs and symptoms of respiratory depression and sedation. (5.4, 7).
- When prescribing, do not convert patients on a mcg per mcg basis from any other oral transmucosal fentanyl product to LAZANDA. (2.1, 5.5)
- When dispensing, do not substitute with any other fentanyl products. (5.5)
- LAZANDA exposes users to risks of addiction, abuse, and misuse, which can lead to overdose and death. Assess patient’s risk before prescribing and monitor regularly for these behaviors and conditions. (5.6)
- LAZANDA is available only through a restricted program called the TIRF REMS. Pharmacies, outpatients, and healthcare professionals who prescribe to outpatients are required to enroll in the program. Patients must be opioid tolerant to receive a TIRF medicine. (5.7)
- Prolonged use of LAZANDA during pregnancy can result in neonatal opioid withdrawal syndrome, which may be life-threatening if not recognized and treated. If prolonged opioid use is required in a pregnant woman, advise the patient of the risk of neonatal opioid withdrawal syndrome and ensure that appropriate treatment will be available. (5.8)

---------------------------RECENT MAJOR CHANGES---------------------------

Boxed Warning 03/2021

Dosage and Administration (2.2) 03/2021

Warnings and Precautions (5.4, 5.6, 5.7) 03/2021

---------------------------INDICATIONS AND USAGE---------------------------

LAZANDA is an opiod agonist indicated for the management of breakthrough pain in cancer patients 18 years of age and older who are already receiving and who are tolerant to around-the-clock opioid therapy for their underlying persistent cancer pain. (1)

Patients considered opioid tolerant are those who are taking, for one week or longer, around-the-clock medicine consisting of at least 60 mg of oral morphine per day, at least 25 mcg of transdermal fentanyl per hour, at least 30 mg of oral oxycodone per day, at least 8 mg of oral hydromorphone per day, at least 25 mg oral oxymorphone per day, at least 60 mg oral hydrocodone per day, or an equianalgesic dose of another opioid daily for a week or longer. Patients must remain on around-the-clock opioids while taking LAZANDA.

Limitations of Use

- Not for use in opioid non-tolerant patients.
- Not for use in the management of acute or postoperative pain, including headache/migraine, dental pain, or in the emergency room.
- As a part of the TIRF REMS, LAZANDA may be dispensed by outpatient pharmacies only to outpatients enrolled in the program (5.7). For inpatient administration of LAZANDA, patient and prescriber enrollment are not required.

-----------------------DOSAGE AND ADMINISTRATION-----------------------

- Patients must require and use around-the-clock opioids when taking LAZANDA. (1)
- Use the lowest effective dose for the shortest duration consistent with individual patient treatment goals (2.1)
- Individualize dosing based on the severity of pain, patient response, prior analgesic experience, and risk factors for addiction, abuse, and misuse. (2.1)
- Initial dose of LAZANDA for all patients is 100 mcg (single spray into one nostril. (2.3)
- Individually titrate to an effective dose, from 100 mcg to 200 mcg to 300 mcg to 400 mcg to 600 mcg, and up to a maximum of 800 mcg, that provides adequate analgesia with tolerable side effects. (2.4)
- Dose is a single spray into one nostril, a single spray into each nostril (2 sprays), three single sprays (alternating nostrils), or two sprays into each nostril (4 sprays); no more than four doses per 24 hours. (2.3, 2.4)
- Wait at least 2 hours before treating another episode of breakthrough pain with LAZANDA. (2.3)
- During any episode, if adequate pain relief is not achieved within 30 minutes, the patient may use a rescue medication as directed by their healthcare provider. (2.4)
- When opioid therapy is no longer required, consider discontinuing LAZANDA along with a gradual downward of other opioids to minimize possible withdrawal effects. (2.7)
- Discuss availability of naloxone with the patient and caregiver and assess each patient’s need for access to naloxone, both when initiating and renewing treatment with LAZANDA. Consider prescribing naloxone based on the patient’s risk factors for overdose [2.2, 5.1, 5.4, 5.6]

-----------------------DOSAGE FORMS AND STRENGTHS-----------------------

- Nasal spray: each spray delivers 100 mcL of solution containing either 100 mcg, 300 mcg or 400 mcg fentanyl base. (3) Supplied in a 5 mL bottle containing 8 sprays.

-----------------------------------CONTRAINDICATIONS-------------------------

- Opioid non-tolerant patients (4)
- Management of acute or postoperative pain including headache/migraine and dental pain, or in emergency department. (4)
- Significant respiratory depression. (4)
- Acute or severe bronchial asthma in an unmonitored setting or in absence of resuscitative equipment. (4)
- Known or suspected gastrointestinal obstruction, including paralytic ileus. (4)
- Known hypersensitivity to fentanyl or components of LAZANDA. (4)

---------------------------WARNINGS AND PRECAUTIONS--------------------

- Life-Threatening Respiratory Depression in Patients with Chronic Pulmonary Disease or in Elderly, Cachectic, or Debilitated Patients: Monitor closely, particularly during initiation and titration. (5.9)
- Serotonin Syndrome: Potentially life-threatening condition could result from concomitant serotonergic drug administration. Discontinue LAZANDA if serotonin syndrome is suspected. (5.10)
- Adrenal Insufficiency: If diagnosed, treat with physiologic replacement of corticosteroids, and wean patient off of the opioid. (5.11)
- Severe Hypotension: Monitor during dosage initiation and titration. Avoid use of LAZANDA in patients with circulatory shock. (5.12)
- Risks of Use in Patients with Increased Intracranial Pressure, Brain Tumors, Head Injury, or Impaired Consciousness: Monitor for sedation and respiratory depression. Avoid use of LAZANDA in patients with impaired consciousness or coma. (5.13)

----------------------------------ADVERSE REACTIONS---------------------------

- Most common adverse reactions (incidence ≥5%) were vomiting, nausea, dizziness, pyrexia, and constipation. (6.1)

To report SUSPECTED ADVERSE REACTIONS, contact West Therapeutic Development, LLC at 1-844-452-9263 or FDA at 1-800-FDA-1088 or www.fda.gov/medwatch.

--------------------------------DRUG INTERACTIONS----------------------------

- Mixed Agonist/Antagonist and Partial Agonist Opioid Analgesics: Avoid use with LAZANDA because they may reduce analgesic effect of LAZANDA or precipitate withdrawal symptoms. (7)

---------------------------USE IN SPECIFIC POPULATIONS---------------------

- Pregnancy: May cause fetal harm. (8.1)
- Lactation: Not Recommended. (8.2)
- Renal and Hepatic Impairment: Administer LAZANDA with caution. (8.6)

See 17 for PATIENT COUNSELING INFORMATION and Medication Guide. Revised: 03/2021

Recent Major Changes Section

Boxed Warning 03/2021

Dosage and Administration (2.2) 03/2021

Warnings and Precautions (5.4) (5.6) (5.7) 03/2021

INDICATIONS AND USAGE

LAZANDA is indicated for the management of breakthrough pain in cancer patients 18 years of age and older who are already receiving and who are tolerant to around-the-clock opioid therapy for their underlying persistent cancer pain.

Patients considered opioid tolerant are those who are taking, for one week or longer, around-the-clock medicine consisting of at least: 60 mg of oral morphine per day, 25 mcg of transdermal fentanyl per hour, 30 mg oral oxycodone per day, 8 mg oral hydromorphone per day, or at least 25 mg oral oxymorphone per day, or at least 60mg oral hydrocodone per day, or an equianalgesic dose of another opioid for a week or longer. Patients must remain on around-the-clock opioids when taking LAZANDA.

Limitations of Use:

- Not for use in opioid non-tolerant patients.
- Not for use in the management of acute or postoperative pain, including headache/migraine, dental pain, or in the emergency department [see Contraindications (4)].
- As a part of the TIRF REMS, LAZANDA may be dispensed by outpatient pharmacies only to outpatients enrolled in the program. [see Warnings and Precautions (5.7)]. For inpatient administration of LAZANDA, patient and prescriber enrollment are not required.

DOSAGE AND ADMINISTRATION

2.1 Important Dosage and Administration Instructions

Healthcare professionals who prescribe LAZANDA for outpatients must enroll in the TIRF REMS and comply with the requirements of the REMS to ensure safe use of

LAZANDA [see Warnings and Precautions (5.7)].

- Use the lowest effective dosage for the shortest duration consistent with individual patient treatment goals.
- It is important to minimize the number of strengths available to patients at any time to prevent confusion and possible overdose.
- Initiate the dosing regimen for each patient individually, taking into account the patient's severity of pain, patient response, prior analgesic treatment experience, and risk factors for addiction, abuse, and misuse.
- Monitor patients closely for respiratory depression, especially within the first 24-72 hours of initiating therapy and following dosage increases with LAZANDA and adjust the dosage accordingly [see Warnings and Precautions (5.1)].
- Instruct patients and caregivers to take steps to store LAZANDA securely and to properly dispose of unused LAZANDA as soon as no longer needed [see Warnings and Precautions (5.2, 5.6), Patient Counseling Information (17)].
- LAZANDA is not bioequivalent with other fentanyl products. Do not convert patients on a mcg per mcg basis from other fentanyl products. There are no conversion directions available for patients on any other fentanyl products (Note: This includes oral, transdermal, or parenteral formulations of fentanyl) [see Warnings and Precautions (5.5)].
- LAZANDA is NOT a generic version of any other oral transmucosal fentanyl product [see Warnings and Precautions (5.5)].

2.2 Patient Access to Naloxone for the Emergency Treatment of Opioid Overdose

Discuss the availability of naloxone for the emergency treatment of opioid overdose with the patient and caregiver and assess the potential need for access to naloxone, both when initiating and renewing treatment with LAZANDA [see Warnings and Precautions (5.1), Patient Counseling Information (17)].

Inform patients and caregivers about the various ways to obtain naloxone as permitted by individual state naloxone dispensing and prescribing requirements or guidelines (e.g., by prescription, directly from a pharmacist, or as part of a community-based program).

Consider prescribing naloxone, based on the patient’s risk factors for overdose, such as concomitant use of CNS depressants, a history of opioid use disorder, or prior opioid overdose. The presence of risk factors for overdose should not prevent the proper management of pain in any given patient [see Warnings and Precautions (5.1, 5.4, 5.6)].

Consider prescribing naloxone if the patient has household members (including children) or other close contacts at risk for accidental ingestion or overdose.

2.3 Initial Dosage

Initiate treatment with LAZANDA for all patients (including those switching from another fentanyl product) using ONE 100 mcg spray of LAZANDA (1 spray in one nostril).

Repeat Dosing

- If adequate analgesia is obtained within 30 minutes of administration of the 100 mcg single spray, treat subsequent episodes of breakthrough pain with this dose.
- If adequate analgesia is not achieved with the first 100 mcg dose, dose escalate in a step-wise manner over consecutive episodes of breakthrough pain until adequate analgesia with tolerable side effects is achieved.
- Patients MUST wait at least 2 hours before treating another episode of breakthrough cancer pain with LAZANDA.

2.4 Titration and Maintenance of Therapy

Titration

The objective of dose titration is to identify an effective and tolerable maintenance dose for ongoing management of breakthrough cancer pain episodes. The effective and tolerable dose of LAZANDA will be determined by dose titration in individual patients.

Titration steps: If adequate analgesia is not achieved with the first 100 mcg dose, dose escalate in a step-wise manner over consecutive episodes of breakthrough pain until adequate analgesia with tolerable side effects is achieved.

Patients MUST wait at least 2 hours before treating another episode of breakthrough cancer pain with LAZANDA.

The titration steps should be:

LAZANDA Dose | How to administer the dose
100 mcg | Using the 100 mcg dose; one spray in one nostril
200 mcg | Using the 100 mcg dose; a total of two sprays, as one spray in each nostril
300 mcg | Using the 100 mcg dose; a total of three sprays, alternating one spray in right nostril, second spray in left nostril, third spray in right nostril
400 mcg | Using the 100 mcg dose, a total of four sprays, alternating one spray in right nostril, second spray in left nostril, third spray in right nostril, and fourth spray in left nostril; OR; Using the 400 mcg dose; one spray in one nostril
600 mcg | Using the 300 mcg dose; total of two sprays, as one spray in each nostril
800 mcg | Using the 400 mcg dose; total of two sprays, as one spray in each nostril

Patients should confirm the dose of LAZANDA that works for them with a second episode of breakthrough pain and review their experience with their physicians to determine if that dose is appropriate, or whether a further adjustment is warranted.

The safety and efficacy of doses higher than 800 mcg have not been evaluated in clinical studies. Avoid the use of a combination of dose strengths to treat an episode as this may cause confusion and dosing errors.

In order to minimize the risk of LAZANDA-related adverse reactions and to identify the appropriate dose, it is imperative that patients be supervised closely by health professionals during the titration process.

Maintenance Therapy

Once an appropriate dose has been established, instruct patients to use that dose for each subsequent breakthrough cancer pain episode. Limit LAZANDA use to four or fewer doses per day.

Patients MUST wait at least 2 hours before treating another episode of breakthrough cancer pain with LAZANDA.

During any episode of breakthrough cancer pain, if there is inadequate pain relief after 30 minutes following LAZANDA dosing or if a separate episode of breakthrough cancer pain occurs before the next dose of LAZANDA is permitted (i.e., within 2 hours), the patients may use a rescue medication as directed by their healthcare provider.

2.5 Dose Re-Adjustment

If the response (analgesia or adverse reactions) to the titrated LAZANDA dose markedly changes, an adjustment of dose may be necessary to ensure that an appropriate dose is maintained.

If more than four episodes of breakthrough pain are experienced per day, re-evaluate the dose of the long-acting opioid used for persistent underlying cancer pain. If the long-acting opioid or dose of long-acting opioid is changed, re-evaluate and re-titrate the LAZANDA dose as necessary to ensure the patient is on an appropriate dose.

Limit the use of LAZANDA to treat four or fewer episodes of breakthrough pain per day.

It is imperative that any dose re-titration is monitored carefully by a healthcare professional.

2.6 Administration of LAZANDA

Instruct patients on the proper use of LAZANDA.

1. Prime the device before use by spraying into the pouch (4 sprays in total). If the product has not been used for 5 days, re-prime by spraying once. For priming, follow the instructions provided [See Medication Guide].
2. Insert the nozzle of the LAZANDA bottle a short distance (about ½ inch or 1 cm) into the nose and point towards the bridge of the nose, tilting the bottle slightly.
3. Press down firmly on the finger grips until they hear a “click” and the number in the counting window advances by one.

Advise patients that the fine mist spray is not always felt on the nasal mucosal membrane and to rely on the audible click and the advancement of the dose counter to confirm a spray has been administered.

2.7 Discontinuation of Therapy

For patients no longer requiring opioid therapy, consider discontinuing LAZANDA along with a gradual downward titration of other opioids to minimize possible withdrawal effects. In patients who continue to take their chronic opioid therapy for persistent pain but no longer require treatment for breakthrough pain, LAZANDA therapy can usually be discontinued immediately [see Drug Abuse and Dependence (9.3)].

2.8 Disposal of LAZANDA

Instruct patients and caregivers to properly dispose of all unused, partially used and used LAZANDA bottles. The remaining liquid in all bottles must be sprayed into the pouch, provided in the pack, for safe disposal as soon as possible.

Instruct the patient how to do this correctly. If there are any unwanted therapeutic sprays remaining in the bottle, instruct the patient to spray these into the pouch until the number “8” appears in the counting window and there are no more full therapeutic sprays obtainable from the bottle. After the counter has advanced to “8”, the patient should continue to push down on the finger grips a total of four times in order to expel any residual medicine from the bottle. After the 8 therapeutic sprays have been emitted, the patient will not hear a click and the counter will not advance beyond “8”; further sprays emitted will not be full sprays and should always be trapped in the pouch, not used therapeutically.

Instruct the patient and caregiver to seal the pouch and place both it and the empty bottle into the child-resistant storage container. Patients must wash their hands with soap and water immediately after handling the pouch.

The patient must discard the child-resistant container containing the pouch and the bottle in the trash.

The patient or caregiver must continue to store the LAZANDA bottle in the specially provided child-resistant container and the pouch out of the reach of children until proper disposal, as described above, is possible.

Instruct the patient to dispose of the LAZANDA bottle and start a new one if it has been 60 days or more since they first used the bottle of LAZANDA.

In the event that caregivers or patients require additional assistance with the disposal of LAZANDA bottles, call the West Therapeutic Development, LLC toll-free number (1-844-452-9263).

DOSAGE FORMS AND STRENGTHS

Nasal Spray, LAZANDA is formulated to deliver a spray of 100 mcL of solution containing 100 mcg, 300 mcg or 400 mcg fentanyl base.

CONTRAINDICATIONS

LAZANDA is contraindicated in:

· Opioid non-tolerant patients: Life-threatening respiratory depression and death could occur at any dose in opioid non-tolerant patients [see Indications and Usage (1); Warnings and Precautions (5.1)].

· Acute or postoperative pain including headache/migraine and dental pain, or in the emergency department.

· Acute or severe bronchial asthma in an unmonitored setting or in the absence of resuscitative equipment [see Warnings and Precautions (5.9)]

· Known or suspected gastrointestinal obstruction, including paralytic ileus [see Warnings and Precautions (5.14)]

Known hypersensitivity to fentanyl or components of LAZANDA (e.g., anaphylaxis, hypersensitivity) [see Adverse Reactions (6.2)].

WARNINGS AND PRECAUTIONS

5.1 Life-Threatening Respiratory Depression

Serious, life-threatening, or fatal respiratory depression has been reported with the use of opioids, even when used as recommended. Respiratory depression, if not immediately recognized and treated, may lead to respiratory arrest and death. Management of respiratory depression may include close observation, supportive measures, and use of opioid antagonists, depending on the patient’s clinical status [see Overdosage (10)]. Carbon dioxide (CO2) retention from opioid-induced respiratory depression can exacerbate the sedating effects of opioids.

While serious, life-threatening, or fatal respiratory depression can occur at any time during the use of LAZANDA, the risk is greatest during the initiation of therapy or following a dosage increase. Monitor patients closely for respiratory depression, especially within the first 24-72 hours of initiating therapy with and following dosage increases of LAZANDA.

To reduce the risk of respiratory depression, proper dosing and titration of LAZANDA are essential [see Dosage and Administration (2.1)]. Overestimating the LAZANDA dosage can result in a fatal overdose with the first dose. The substitution of LAZANDA for any other fentanyl product may result in fatal overdose [see Warnings and Precautions (5.5)].

LAZANDA could be fatal to individuals for whom it is not prescribed and for those who are not opioid-tolerant.

Accidental ingestion of (or exposure to) even one dose of LAZANDA, especially by (in) children, can result in respiratory depression and death due to an overdose of fentanyl [see Warnings and Precautions (5.2)].

Educate patients and caregivers on how to recognize respiratory depression and emphasize the importance of calling 911 or getting emergency medical help right away in the event of a known or suspected overdose [see Patient Counseling Information (17)].

Opioids can cause sleep-related breathing disorders including central sleep apnea (CSA) and sleep-related hypoxemia. Opioid use increases the risk of CSA in a dose-dependent fashion. In patients who present with CSA, consider decreasing the opioid dosage using best practices for opioid taper [ see Dosage and Administration (2.5)].

Patient Access to Naloxone for the Emergency Treatment of Opioid Overdose

Discuss the availability of naloxone for the emergency treatment of opioid overdose with the patient and caregiver and assess the potential need for access to naloxone, both when initiating and renewing treatment with LAZANDA. Inform patients and caregivers about the various ways to obtain naloxone as permitted

by individual state naloxone dispensing and prescribing requirements or guidelines (e.g., by prescription, directly from a pharmacist, or as part of a community-based program). Educate patients and caregivers on how to recognize respiratory depression and emphasize the importance of calling 911 or getting emergency medical help, even if naloxone is administered [see Patient Counseling Information (17)].

Consider prescribing naloxone, based on the patient’s risk factors for overdose, such as concomitant use of CNS depressants, a history of opioid use disorder, or prior opioid overdose. The presence of risk factors for overdose should not prevent the proper management of pain in any given patient. Also consider prescribing naloxone if the patient has household members (including children) or other close contacts at risk for accidental ingestion or overdose. If naloxone is prescribed, educate patients and caregivers on how to treat with naloxone. [see Warnings and Precautions (5.4, 5.6), Patient Counseling Information (17)].

5.2 Increased Risk of Overdose in Children Due to Accidental Ingestion or Exposure

Death has been reported in children who have accidentally ingested transmucosal immediate –release fentanyl products.

Patients and their caregivers must be informed that LAZANDA contains a medicine in an amount which can be fatal to a child. Physicians and dispensing pharmacists must specifically question patients or caregivers about the presence of children in the home (on a full time or visiting basis) and counsel them regarding the dangers to children from inadvertent exposure.

Patients and their caregivers must be instructed to keep both used and unused dosage units out of the reach of children. While all units should be disposed of immediately after use, partially consumed units represent a special risk to children. In the event that a unit is not completely consumed it must be properly disposed as soon as possible [see Patient Counseling Information (17)].

Detailed instructions for the proper storage, administration, disposal, and important instructions for managing an overdose of LAZANDA are provided in the LAZANDA Medication Guide. Encourage patients to read this information in its entirety and give them an opportunity to have their questions answered.

5.3 Risks of Concomitant Use or Discontinuation of Cytochrome P450 3A4 Inhibitors and Inducers

Concomitant use of LAZANDA with a CYP3A4 inhibitor, such as macrolide antibiotics (e.g., erythromycin), azole-antifungal agents (e.g., ketoconazole), and protease inhibitors (e.g., ritonavir), may increase plasma concentrations of fentanyl and prolong opioid adverse reactions, which may cause potentially fatal respiratory depression [see Warnings and Precautions (5.2)], particularly when an inhibitor is added after a stable dose of LAZANDA is achieved. Similarly, discontinuation of a CYP3A4 inducer, such as rifampin, carbamazepine, and phenytoin, in LAZANDA treated patients may increase fentanyl plasma concentrations and prolong opioid adverse reactions. When using LAZANDA with CYP3A4 inhibitors or discontinuing CYP3A4 inducers in LAZANDA treated patients, monitor patients closely at frequent intervals and consider dosage reduction of LAZANDA until stable drug effects are achieved [see Dosage and Administration (2.4), Drug Interactions (7)].

Concomitant use of LAZANDA with CYP3A4 inducers or discontinuation of an CYP3A4 inhibitor could decrease fentanyl plasma concentrations, decrease opioid efficacy or, possibly, lead to a withdrawal syndrome in a patient who had developed physical dependence to fentanyl. When using LAZANDA with CYP3A4 inducers or discontinuing CYP3A4 inhibitors, monitor patients closely at frequent intervals and consider increasing the opioid dosage if needed to maintain adequate analgesia or if symptoms of opioid withdrawal occur [see Drug Interactions (7)].

5.4 Risks from Concomitant Use with Benzodiazepines or Other CNS Depressants

Profound sedation, respiratory depression, coma, and death may result from the concomitant use of LAZANDA with benzodiazepines or other CNS depressants (e.g., non-benzodiazepine sedatives/hypnotics, anxiolytics, tranquilizers, muscle relaxants, general anesthetics, antipsychotics, other opioids, alcohol). Because of these risks, reserve concomitant prescribing of these drugs for use in patients for whom alternative treatment options are inadequate.

Observational studies have demonstrated that concomitant use of opioid analgesics and benzodiazepines increases the risk of drug-related mortality compared to use of opioid analgesics alone. Because of similar pharmacological properties, it is reasonable to expect similar risk with the concomitant use of other CNS depressant drugs with opioid analgesics [see Drug Interactions (7)].

If the decision is made to prescribe a benzodiazepine or other CNS depressant concomitantly with an opioid analgesic, prescribe the lowest effective dosages and minimum durations of concomitant use. In patients already receiving an opioid analgesic, prescribe a lower initial dose of the benzodiazepine or other CNS depressant than indicated in the absence of an opioid, and titrate based on clinical response. If an opioid analgesic is initiated in a patient already taking a benzodiazepine or other CNS depressant, prescribe a lower initial dose of the opioid analgesic, and titrate based on clinical response. Follow patients closely for signs and symptoms of respiratory depression and sedation.

If concomitant use is warranted, consider prescribing naloxone for the emergency treatment of opioid overdose [see Dosage and Administration (2.2), Warnings and Precautions (5.1)].

Advise both patients and caregivers about the risks of respiratory depression and sedation when LAZANDA is used with benzodiazepines or other CNS depressants (including alcohol and illicit drugs). Advise patients not to drive or operate heavy machinery until the effects of concomitant use of the benzodiazepine or other CNS depressant have been determined. Screen patients for risk of substance use disorders, including opioid abuse and misuse, and warn them of the risk for overdose and death associated with the use of additional CNS depressants including alcohol and illicit drugs [see Drug Interactions (7), Patient Counseling Information (17)].

5.5 Risk of Medication Errors

When prescribing, DO NOT convert a patient to LAZANDA from any other fentanyl product on a mcg per mcg basis as LAZANDA and other fentanyl products are not equivalent on a microgram per microgram basis.

LAZANDA is NOT a generic version of other transmucosal immediate release fentanyl (TIRF) formulations. When dispensing, DO NOT substitute a LAZANDA prescription for any other TIRF formulation under any circumstances. Other TIRF formulations and LAZANDA are not equivalent. Substantial differences exist in the pharmacokinetic profile of LAZANDA compared to other fentanyl products including other TIRF formulations that result in clinically important differences in the rate and extent of absorption of fentanyl. As a result of these differences, the substitution of LAZANDA for any other fentanyl product may result in a fatal overdose.

There are no safe conversion directions available for patients on any other fentanyl products. (Note: This includes oral, transdermal, or parenteral formulations of fentanyl.) Therefore, for opioid tolerant patients, the initial dose of LAZANDA should always be ONE 100 mcg spray. Each patient should be individually titrated to provide adequate analgesia while minimizing side effects [see Dosage and Administration (2.4)].

5.6 Addiction, Abuse, and Misuse

LAZANDA contains fentanyl a Schedule II controlled substance. As an opioid, LAZANDA exposes users to the risks of addiction, abuse, and misuse [see Drug Abuse and Dependence (9)].

Although the risk of addiction in any individual is unknown, it can occur in patients appropriately prescribed LAZANDA. Addiction can occur at recommended dosages and if the drug is misused or abused.

Assess each patient’s risk for opioid addiction, abuse, or misuse prior to prescribing LAZANDA, and monitor all patients receiving LAZANDA for the development of these behaviors and conditions. Risks are increased in patients with a personal or family history of substance abuse (including drug or alcohol abuse or addiction) or mental illness (e.g., major depression). The potential for these risks should not, however, prevent the proper management of pain in any given patient. Patients at increased risk may be prescribed opioids such as LAZANDA, but use in such patients necessitates intensive counseling about the risks and proper use of LAZANDA along with intensive monitoring for signs of addiction, abuse, and misuse. Consider prescribing naloxone for the emergency treatment of opioid overdose [see Dosage and Administration (2.2), Warnings and Precautions (5.1)].

Opioids are sought by drug abusers and people with addiction disorders and are subject to criminal diversion. Consider these risks when prescribing or dispensing LAZANDA. Strategies to reduce these risks include prescribing the drug in the smallest appropriate quantity and advising the patient on the proper disposal of unused drug [see Patient Counseling Information (17)]. Contact local state professional licensing board or state controlled substances authority for information on how to prevent and detect abuse or diversion of this product.

5.7 Transmucosal Immediate Release Fentanyl (TIRF) Risk Evaluation and Mitigation Strategy (REMS)

Because of the risk for accidental exposure, misuse, abuse, addiction, and overdose [see Warnings and Precautions (5.6)], LAZANDA is available only through a restricted program under a REMS called the TIRF REMS. Under the TIRF REMS, healthcare professionals who prescribe to outpatients, the outpatients themselves, and pharmacies are required to enroll in the program.

Notable requirements of the TIRF REMS are:

- Prescribers for outpatient use must must be certified by the TIRF REMS program by enrolling and completing training. Prescribers must document opioid tolerance with every LAZANDA prescription.
- Outpatients must be enrolled in the REMS program, and must be opiod tolerant to receive LAZANDA [see Dosage and Administration (2.1)]
- Outpatient pharmacies must be certified with the REMS program and verify documentation of opioid tolerance with every LAZANDA prescription.
- Inpatient pharmacies must be certified with the REMS program and develop policies and procedures to verify opioid tolerance in inpatients who require LAZANDA while hospitalized.
- Wholesalers and distributers must enroll in the REMS program and distribute only to certified pharmacies.
- Further information, including a list of certified pharmacies and enrolled distributors, is available at www.tirfremsaccess.com or by calling 1-866-822-1483.

5.8 Neonatal Opioid Withdrawal Syndrome

Prolonged use of LAZANDA during pregnancy can result in withdrawal in the neonate. Neonatal opioid withdrawal syndrome, unlike opioid withdrawal syndrome in adults, may be life-threatening if not recognized and treated, and requires management according to protocols developed by neonatology experts. Observe newborns for signs of neonatal opioid withdrawal syndrome and manage accordingly. Advise pregnant women using opioids for a prolonged period of the risk of neonatal opioid withdrawal syndrome and ensure that appropriate treatment will be available [see Use in Specific Populations (8.1), Patient Counseling Information (17)].

5.9 Life-Threatening Respiratory Depression in Patients with Chronic Pulmonary Disease or in Elderly, Cachectic, or Debilitated Patients

The use of LAZANDA in patients with acute or severe bronchial asthma in an unmonitored setting or in the absence of resuscitative equipment is contraindicated.

Patients with Chronic Pulmonary Disease: LAZANDA-treated patients with significant chronic obstructive pulmonary disease or cor pulmonale, and those with a substantially decreased respiratory reserve, hypoxia, hypercapnia, or pre-existing respiratory depression are at increased risk of decreased respiratory drive including apnea, even at recommended dosages of LAZANDA [see Warnings and Precautions (5.1)].

Elderly, Cachectic, or Debilitated Patients: Life-threatening respiratory depression is more likely to occur in elderly, cachectic, or debilitated patients because they may have altered pharmacokinetics or altered clearance compared to younger, healthier patients [see Warnings and Precautions (5.1)].

Monitor such patients closely, particularly when initiating and titrating LAZANDA and when LAZANDA is given concomitantly with other drugs that depress respiration [see Warnings and Precautions (5.1)]. Alternatively, consider the use of non-opioid analgesics in these patients.

5.10 Serotonin Syndrome with Concomitant Use of Serotonergic Drugs

Cases of serotonin syndrome, a potentially life-threatening condition, have been reported during concomitant use of fentanyl with serotonergic drugs. Serotonergic drugs include selective serotonin reuptake inhibitors (SSRIs), serotonin and norepinephrine reuptake inhibitors (SNRIs), tricyclic antidepressants (TCAs), triptans, 5-HT3 receptor antagonists, drugs that affect the serotonergic neurotransmitter system (e.g., mirtazapine, trazodone, tramadol), certain muscle relaxants (i.e., cyclobenzaprine, metaxalone), and drugs that impair metabolism of serotonin (including MAO inhibitors, both those intended to treat psychiatric disorders and also others, such as linezolid and intravenous methylene blue) [see Drug Interactions (7)]. This may occur within the recommended dosage range.

Serotonin syndrome symptoms may include mental status changes (e.g., agitation, hallucinations, coma), autonomic instability (e.g., tachycardia, labile blood pressure, hyperthermia), neuromuscular aberrations (e.g., hyperreflexia, incoordination, rigidity), and/or gastrointestinal symptoms (e.g., nausea, vomiting, diarrhea). The onset of symptoms generally occurs within several hours to a few days of concomitant use, but may occur later than that. Discontinue LAZANDA if serotonin syndrome is suspected.

5.11 Adrenal Insufficiency

Cases of adrenal insufficiency have been reported with opioid use, more often following greater than one month of use. Presentation of adrenal insufficiency may include non-specific symptoms and signs including nausea, vomiting, anorexia, fatigue, weakness, dizziness, and low blood pressure. If adrenal insufficiency is suspected, confirm the diagnosis with diagnostic testing as soon as possible. If adrenal insufficiency is diagnosed, treat with physiologic replacement doses of corticosteroids. Wean the patient off of the opioid to allow adrenal function to recover and continue corticosteroid treatment until adrenal function recovers. Other opioids may be tried as some cases reported use of a different opioid without recurrence of adrenal insufficiency. The information available does not identify any particular opioids as being more likely to be associated with adrenal insufficiency.

5.12 Severe Hypotension

LAZANDA may cause severe hypotension including orthostatic hypotension and syncope in ambulatory patients. There is increased risk in patients whose ability to maintain blood pressure has already been compromised by a reduced blood volume or concurrent administration of certain CNS depressant drugs (e.g. phenothiazines or general anesthetics) [see Drug Interactions (7)]. Monitor these patients for signs of hypotension after initiating or titrating the dosage of LAZANDA. In patients with circulatory shock, LAZANDA may cause vasodilation that can further reduce cardiac output and blood pressure. Avoid the use of LAZANDA in patients with circulatory shock.

5.13 Risks of Use in Patients with Increased Intracranial Pressure, Brain Tumors, Head Injury, or Impaired Consciousness

In patients who may be susceptible to the intracranial effects of CO2 retention (e.g., those with evidence of increased intracranial pressure or brain tumors), LAZANDA may reduce respiratory drive, and the resultant CO2 retention can further increase intracranial pressure. Monitor such patients for signs of sedation and respiratory depression, particularly when initiating therapy with LAZANDA.

Opioids may also obscure the clinical course in a patient with a head injury. Avoid the use of LAZANDA in patients with impaired consciousness or coma.

5.14 Risks of Use in Patients with Gastrointestinal Conditions

LAZANDA is contraindicated in patients with known or suspected gastrointestinal obstruction, including paralytic ileus.

The fentanyl in LAZANDA may cause spasm of the sphincter of Oddi. Opioids may cause increases in serum amylase. Monitor patients with biliary tract disease, including acute pancreatitis for worsening symptoms.

5.15 Increased Risk of Seizures in Patients with Seizure Disorders

The fentanyl in LAZANDA may increase the frequency of seizures in patients with seizure disorders, and may increase the risk of seizures occurring in other clinical settings associated with seizures. Monitor patients with a history of seizure disorders for worsened seizure control during LAZANDA therapy.

5.16 Risks of Driving and Operating Machinery

LAZANDA may impair the mental or physical abilities needed to perform potentially hazardous activities such as driving a car or operating machinery. Warn patients not to drive or operate dangerous machinery unless they are tolerant to the effects of LAZANDA and know how they will react to the medication.

5.17 Cardiac Disease

Intravenous fentanyl may produce bradycardia. Therefore, use LAZANDA with caution in patients with bradyarrhythmias.

ADVERSE REACTIONS

6.1 Clinical Studies Experience

Because clinical trials are conducted under widely varying conditions, adverse event rates observed in the clinical trials of a drug product cannot be directly compared to rates in the clinical trials of another drug and may not reflect the rates observed in practice.

The safety of LAZANDA has been evaluated in a total of 523 opioid-tolerant patients with breakthrough cancer pain. The average duration of therapy in patients in the long-term study was 73 days, with 153 patients being treated for over 3 months. Patients continuing into the open-label extension period of the safety study have been treated for up to 26 months.

The clinical trials of LAZANDA were designed to evaluate safety and efficacy in treating breakthrough cancer pain; all patients were also taking concomitant opioids, such as sustained-release morphine, sustained-release oxycodone, or transdermal fentanyl, for their persistent cancer pain. The adverse reaction data presented in Table 1 reflect the actual percentage of patients experiencing each adverse effect among patients who received LAZANDA for breakthrough cancer pain along with a concomitant opioid for persistent cancer pain. There has been no attempt to correct for concomitant use of other opioids, duration of LAZANDA therapy, or cancer-related symptoms. Adverse events are included regardless of causality or severity. Table 1 lists adverse reactions with an overall frequency of 5% or greater within the total population that occurred during titration by maximum dose received. The ability to assign LAZANDA a dose-response relationship to these adverse events is limited by the titration schemes used in these studies.

Table 1: Adverse Reactions That Occurred During Titration at a Frequency of >5%

System Organ Class MedDRA preferred term, n (%) | 100 mcg; (N=483) | 200 mcg; (N=380) | 400 mcg; (N=301) | 800 mcg; (N=161) | Total; (N=516)
Gastrointestinal disorders
Nausea | 19 (4) | 6 (2) | 6 (2) | 5 (3) | 35 (7)
Vomiting | 14 (3) | 10 (3) | 9 (3) | 1 (1) | 33 (6)
Nervous system disorders
Dizziness | 14 (3) | 11 (3) | 6 (2) | 4 (2) | 31 (6)

Table 2 lists, by dose, adverse reactions with an overall frequency of ≥5% within the total population that occurred after a final titrated dose had been determined.

Table 2: Adverse Reactions That Occurred During Maintenance Treatment at a Frequency of ≥5%

System Organ Class MedDRA preferred term, n (%) | 100 mcg; (N=61) | 200 mcg; (N=68) | 400 mcg; (N=109) | 800 mcg; (N=108) | Total; (N=346)
Gastrointestinal disorders
Vomiting | 8 (13) | 5 (7) | 9 (8) | 12 (11) | 34 (10)
Nausea | 4 (7) | 6 (9) | 4 (4) | 9 (8) | 23 (7)
Constipation | 6 (10) | 1 (1) | 8 (7) | 5 (5) | 20 (6)
General disorders and administration site conditions
Pyrexia | 3 (5) | 5 (7) | 8 (7) | 6 (6) | 22 (6)

The adverse reactions listed below represent those that occurred in ≥1% of patients from clinical trials while receiving LAZANDA. Events are classified by system organ class.

Eye disorders: dry eye, swelling, ptosis, strabismus

Blood and Lymphatic System Disorders: anemia, neutropenia

Cardiac Disorders: cardiorespiratory arrest

Gastrointestinal Disorders: vomiting, nausea, constipation, diarrhea, abdominal pain, gastritis, ascites, dry mouth, dyspepsia, mouth ulcer, proctalgia

General Disorders and Administration Site Conditions: pyrexia, fatigue, edema peripheral, asthenia, edema

Hepatobiliary Disorders: jaundice

Immune System Disorders: hypersensitivity

Infections and Infestations: urinary tract infection, pneumonia, nasopharyngitis, infection, rhinitis, upper respiratory tract infection, bronchitis

Injury, Poisoning and Procedural Complications: fall

Investigations: weight decreased, blood alkaline phosphatase increased

Metabolism and Nutrition Disorders: dehydration, decreased appetite, hyperglycemia, anorexia

Musculoskeletal and Connective Tissue Disorders: back pain, pain in extremity, arthralgia

Nervous System Disorders: dizziness, somnolence, headache, dysgeusia

Psychiatric Disorders: anxiety, insomnia, depression, confusional state, disorientation, agitation

Respiratory, Thoracic and Mediastinal Disorders: dyspnea, epistaxis, cough, pharyngolaryngeal pain, nasal discomfort, rhinorrhea, nasal congestion, postnasal drip, pulmonary embolism

Skin and Subcutaneous Tissue Disorders: pruritus, hyperhidrosis, decubitus ulcer, mouth ulceration

Vascular Disorders: hypertension, deep vein thrombosis

6.2 Postmarketing Experience

The following adverse reactions have been identified during post approval use fentanyl. Because these reactions are reported voluntarily from a population of uncertain size, it is not always possible to reliably estimate their frequency or establish a causal relationship to drug exposure.

Serotonin syndrome: Cases of serotonin syndrome, a potentially life-threatening condition, have been reported during concomitant use of opioids with serotonergic drugs.

Adrenal insufficiency: Cases of adrenal insufficiency have been reported with opioid use, more often following greater than one month of use.

Anaphylaxis: Anaphylaxis has been reported with ingredients contained in LAZANDA.

Androgen deficiency: Cases of androgen deficiency have occurred with chronic use of opioids [see Clinical Pharmacology (12.2)].

DRUG INTERACTIONS

Table 3 includes clinically significant drug interactions with LAZANDA.

Table 3: Clinically Significant Drug Interactions with LAZANDA

Inhibitors of CYP3A4
Clinical Impact: | The concomitant use of LAZANDA and CYP3A4 inhibitors can increase the plasma concentration of fentanyl, resulting in increased or prolonged opioid effects, particularly when an inhibitor is added after a stable dose of LAZANDA is achieved [see Warnings and Precautions (5.4)].; After stopping a CYP3A4 inhibitor, as the effects of the inhibitor decline, the fentanyl plasma concentration will decrease [see Clinical Pharmacology (12.3)], resulting in decreased opioid efficacy or a withdrawal syndrome in patients who had developed physical dependence to fentanyl.
Intervention: | If concomitant use is necessary, consider dosage reduction of LAZANDA until stable drug effects are achieved. Monitor patients for respiratory depression and sedation at frequent intervals.; If a CYP3A4 inhibitor is discontinued, consider increasing the LAZANDA dosage until stable drug effects are achieved. Monitor for signs of opioid withdrawal.
Examples | Macrolide antibiotics (e.g., erythromycin), azole-antifungal agents (e.g. ketoconazole), protease inhibitors (e.g., ritonavir), grapefruit juice
CYP3A4 Inducers
Clinical Impact: | The concomitant use of LAZANDA and CYP3A4 inducers can decrease the plasma concentration of fentanyl [see Clinical Pharmacology (12.3)], resulting in decreased efficacy or onset of a withdrawal syndrome in patients who have developed physical dependence to fentanyl [see Warnings and Precautions (5.18)].; After stopping a CYP3A4 inducer, as the effects of the inducer decline, the fentanyl plasma concentration will increase [see Clinical Pharmacology (12.3)], which could increase or prolong both the therapeutic effects and adverse reactions, and may cause serious respiratory depression.
Intervention: | If concomitant use is necessary, consider increasing the LAZANDA dosage until stable drug effects are achieved. Monitor for signs of opioid withdrawal. If a CYP3A4 inducer is discontinued, consider LAZANDA dosage reduction and monitor for signs of respiratory depression.
Examples | Rifampin, carbamazepine, phenytoin
Benzodiazepines and Other Central Nervous System (CNS) Depressants
Clinical Impact: | Due to additive pharmacologic effect, the concomitant use of benzodiazepines and other CNS depressants, including alcohol, can increase the risk of hypotension, respiratory depression, profound sedation, coma, and death.
Intervention: | Reserve concomitant prescribing of these drugs for use in patients for whom alternative treatment options are inadequate. Limit dosages and durations to the minimum required. Follow patients closely for signs of respiratory depression and sedation [see Warnings and Precautions (5.4)].; If concomitant use is warranted, consider prescribing naloxone for the emergency treatment of opioid overdose [see Dosage and Administration (2.2), Warnings and Precautions (5.1, 5.4, 5.6)].
Examples: | Benzodiazepines and other sedatives/hypnotics, anxiolytics, tranquilizers, muscle relaxants, general anesthetics, antipsychotics, other opioids, alcohol.
Serotonergic Drugs
Clinical Impact: | The concomitant use of opioids with other drugs that affect the serotonergic neurotransmitter system has resulted in serotonin syndrome [see Warnings and Precautions 5.10].
Intervention: | If concomitant use is warranted, carefully observe the patient, particularly during treatment initiation and dose adjustment. Discontinue LAZANDA if serotonin syndrome is suspected.
Examples: | Selective serotonin reuptake inhibitors (SSRIs), serotonin and norepinephrine reuptake inhibitors (SNRIs), tricyclic antidepressants (TCAs), triptans, 5-HT3 receptor antagonists, drugs that effect the serotonin neurotransmitter system (e.g., mirtazapine, trazodone, tramadol), certain muscle relaxants (i.e., cyclobenzaprine, metaxalone), monoamine oxidase (MAO) inhibitors (those intended to treat psychiatric disorders and also others, such as linezolid and intravenous methylene blue).
Monoamine Oxidase Inhibitors (MAOIs)
Clinical Impact: | MAOI interactions with opioids may manifest as serotonin syndrome [see Warnings and Precautions (5.10)] or opioid toxicity (e.g., respiratory depression, coma) [see Warnings and Precautions (5.1)].
Intervention: | The use of LAZANDA is not recommended for patients taking MAOIs or within 14 days of stopping such treatment.
Examples: | phenelzine, tranylcypromine, linezolid
Mixed Agonist/Antagonist and Partial Agonist Opioid Analgesics
Clinical Impact: | May reduce the analgesic effect of LAZANDA and/or precipitate withdrawal symptoms.
Intervention: | Avoid concomitant use.
Examples: | butorphanol, nalbuphine, pentazocine, buprenorphine,
Muscle Relaxants
Clinical Impact: | fentanyl may enhance the neuromuscular blocking action of skeletal muscle relaxants and produce an increased degree of respiratory depression.
Intervention: | Monitor patients for signs of respiratory depression that may be greater than otherwise expected and decrease the dosage of LAZANDA and/or the muscle relaxant as necessary. Due to the risk of respiratory depression with concomitant use of skeletal muscle relaxants and opioids, consider prescribing naloxone for the emergency treatment of opioid overdose [see Dosage and Administration (2.2), Warnings and Precautions (5.1, 5.4)]
Examples: | cyclobenzaprine, metaxalone
Diuretics
Clinical Impact: | Opioids can reduce the efficacy of diuretics by inducing the release of antidiuretic hormone.
Intervention: | Monitor patients for signs of diminished diuresis and/or effects on blood pressure and increase the dosage of the diuretic as needed.
Anticholinergic Drugs
Clinical Impact: | The concomitant use of anticholinergic drugs may increase risk of urinary retention and/or severe constipation, which may lead to paralytic ileus.
Intervention: | Monitor patients for signs of urinary retention or reduced gastric motility when LAZANDA is used concomitantly with anticholinergic drugs.
Agents used to treat Allergic Rhinitis
Clinical Impact: | The presence of allergic rhinitis is not expected to affect LAZANDA absorption. However, co-administration of a vasoconstrictive nasal decongestant such as oxymetazoline to treat allergic rhinitis leads to lower peak plasma concentrations and a delayed Tmax of fentanyl that may cause LAZANDA to be less effective in patients with allergic rhinitis who use such decongestants, thus potentially impairing pain management. Additionally, in view of the possibility that the titration of a patient while they are experiencing an acute episode of rhinitis could lead to incorrect dose identification (particularly if they are using a vasoconstrictive decongestant), titration under these circumstances must be avoided [see Clinical Pharmacology (12.3)].
Intervention: | Avoid using LAZANDA in patients with allergic rhinitis and consider other products with a different route of administration.

USE IN SPECIFIC POPULATIONS

2

8.1 Pregnancy

Risk Summary

Prolonged use of opioid analgesics during pregnancy may cause neonatal opioid withdrawal syndrome. Available data with LAZANDA in pregnant women are insufficient to inform a drug-associated risk for major birth defects and miscarriage.

In animal reproduction studies fentanyl administration to pregnant rats during organogenesis was embryocidal at doses within the range of the human recommended dosing for LAZANDA. No evidence of malformations were noted in animal studies completed to date [ see Data].

The estimated background risk of major birth defects and miscarriage for the indicated population is unknown. All pregnancies have a background risk of birth defect, loss, or other adverse outcomes. In the U.S. general population, the estimated background risk of major birth defects and miscarriage in clinically recognized pregnancies is 2-4% and 15-20%, respectively.

Clinical Considerations

Fetal/Neonatal Adverse Reactions

Prolonged use of opioid analgesics during pregnancy for medical or nonmedical purposes can result in physical dependence in the neonate and neonatal opioid withdrawal syndrome shortly after birth.

Neonatal opioid withdrawal syndrome presents as irritability, hyperactivity and abnormal sleep pattern, high pitched cry, tremor, vomiting, diarrhea and failure to gain weight. The onset, duration, and severity of neonatal opioid withdrawal syndrome vary based on the specific opioid used, duration of use, timing and amount of last maternal use, and rate of elimination of the drug by the newborn. Observe newborns for symptoms of neonatal opioid withdrawal syndrome and manage accordingly [see Warnings and Precautions (5.3)].

Labor or Delivery

Opioids cross the placenta and may produce respiratory depression and psycho-physiologic effects in neonates. An opioid antagonist, such as naloxone, must be available for reversal of opioid-induced respiratory depression in the neonate. LAZANDA is not recommended for use in pregnant women during or immediately prior to labor, when other analgesic techniques are more appropriate. Opioid analgesics, including LAZANDA, can prolong labor through actions which temporarily reduce the strength, duration, and frequency of uterine contractions. However, this effect is not consistent and may be offset by an increased rate of cervical dilation, which tends to shorten labor. Monitor neonates exposed to opioid analgesics during labor for signs of excess sedation and respiratory depression.

Data

Human Data

In women treated acutely with intravenous or epidural fentanyl during labor, symptoms of neonatal respiratory or neurological depression were no more frequent than would be expected in infants of untreated mothers.

Transient neonatal muscular rigidity has been observed in infants whose mothers were treated with intravenous fentanyl.

Animal Data

Fentanyl has been shown to embryocidal in pregnant rats at doses of 30 mcg/kg intravenously (0.4 times the 800 mcg dose of LAZANDA on a mg/m^2 basis) and 160 mcg/kg subcutaneously (2 times the 800 mcg dose of LAZANDA based on a mg/m^2 basis). There was no evidence of teratogenicity reported.

No evidence of malformations or adverse effects on the fetus was reported in a published study in which pregnant rats were administered fentanyl continuously via subcutaneously implanted osmotic minipumps at doses of 10, 100, or 500 mcg/kg/day starting 2-weeks prior to breeding and throughout pregnancy. The high dose was approximately 6 times the human dose of 800 mcg LAZANDA per pain episode on a mg/m^2 basis and produced mean steady-state plasma levels that are 3 times higher than the mean Cmax observed following administration of 800 mcg dose of LAZANDA in humans.

8.2 Lactation

Risk Summary

Fentanyl is present in breast milk. One published lactation study reports a relative infant dose of fentanyl of 0.024%. However, there is insufficient information to determine the effects of fentanyl on the breastfed infant and the effects of fentanyl on milk production.

Because of the potential for serious adverse reactions, including excess sedation and respiratory depression in a breastfed infant, advise patients that breastfeeding is not recommended during treatment with LAZANDA.

Clinical Considerations

Monitor infants exposed to LAZANDA through breast milk for excess sedation and respiratory depression. Withdrawal symptoms can occur in breastfed infants when maternal administration of an opioid analgesic is stopped, or when breast-feeding is stopped.

8.3 Females and Males of Reproductive Potential

Chronic use of opioids may cause reduced fertility in females and males of reproductive potential. It is not known whether these effects on fertility are reversible [see Adverse Reactions (6.2), Clinical Pharmacology (12.2), Nonclinical Toxicology(13.1)].

8.4 Pediatric Use

The safety and efficacy of LAZANDA have not been established in patients below the age of 18 years.

8.5 Geriatric Use

Of the 523 opioid tolerant cancer patients with breakthrough cancer pain in clinical studies of LAZANDA, 148 (28%) were aged 60 years and over. No clinically meaningful difference was noted in the safety profile of the group aged over 60 years versus that of younger patients in LAZANDA clinical trials.

Elderly patients have been shown to be more sensitive to the effects of fentanyl when administered intravenously compared with the younger population. Therefore, exercise caution when individually titrating LAZANDA in elderly patients to provide adequate efficacy while minimizing risk.

Respiratory depression is the chief risk for elderly patients treated with opioids, and has occurred after large initial doses were administered to patients who were not opioid-tolerant or when opioids were co-administered with other agents that depress respiration. Titrate the dosage of LAZANDA slowly in geriatric patients and monitor closely for signs of central nervous system and respiratory depression [see Warnings and Precautions (5.1)].

Fentanyl is known to be substantially excreted by the kidney, and the risk of adverse reactions to this drug may be greater in patients with impaired renal function. Because elderly patients are more likely to have decreased renal function, care should be taken in dose selection, and it may be useful to monitor renal function.

8.6 Patients with Renal or Hepatic Impairment

Insufficient information exists to make recommendations regarding the use of LAZANDA in patients with impaired renal or hepatic function. Fentanyl is metabolized primarily via the human CYP3A4 isoenzyme system and the inactive metabolite is mostly eliminated in urine. If the drug is used in these patients, it is to be used with caution because of the hepatic metabolism and renal excretion of fentanyl.

It is recommended that LAZANDA be titrated to clinical effect for all patients with special care taken in patients with severe renal or hepatic disease.

8.7 Sex

Both male and female opioid-tolerant cancer patients were studied for the treatment of breakthrough cancer pain. No clinically relevant sex differences were observed in adverse events.

8.8 Patients with Allergic (Seasonal) Rhinitis

The pharmacokinetic and safety profiles of LAZANDA in individuals with known allergic (seasonal) rhinitis showed no clinically meaningful differences in rate or extent of exposure to fentanyl, or in local tolerability of LAZANDA when compared to Asymptomatic (Unchallenged) state. However, when treated for their rhinitis with oxymetazoline, LAZANDA absorption was compromised [see Pharmacokinetics (12.3)].

DRUG ABUSE AND DEPENDENCE

9.1 Controlled Substance

LAZANDA contains fentanyl, a Schedule II controlled substance.

9.2 Abuse

LAZANDA contains fentanyl, a substance with a high potential for abuse similar to other opioids including hydrocodone, hydromorphone, methadone, morphine, oxycodone, oxymorphone, and tapentadol. LAZANDA can be abused and is subject to misuse, addiction, and criminal diversion [see Warnings and Precautions (5.6)].

All patients treated with opioids require careful monitoring for signs of abuse and addiction, since use of opioid analgesic products carries the risk of addiction even under appropriate medical use.

Prescription drug abuse is the intentional non-therapeutic use of a prescription drug, even once, for its rewarding psychological or physiological effects.

Drug addiction is a cluster of behavioral, cognitive, and physiological phenomena that develop after repeated substance use and includes: a strong desire to take the drug, difficulties in controlling its use, persisting in its use despite harmful consequences, a higher priority given to drug use than to other activities and obligations, increased tolerance, and sometimes a physical withdrawal.

“Drug-seeking” behavior is very common in persons with substance use disorders. Drug-seeking tactics include emergency calls or visits near the end of office hours, refusal to undergo appropriate examination, testing, or referral, repeated “loss” of prescriptions, tampering with prescriptions, and reluctance to provide prior medical records or contact information for other treating health care provider(s). “Doctor shopping” (visiting multiple prescribers to obtain additional prescriptions) is common among drug abusers and people suffering from untreated addiction. Preoccupation with achieving adequate pain relief can be appropriate behavior in a patient with poor pain control.

Abuse and addiction are separate and distinct from physical dependence and tolerance. Health care providers should be aware that addiction may not be accompanied by concurrent tolerance and symptoms of physical dependence in all addicts. In addition, abuse of opioids can occur in the absence of true addiction.

LAZANDA, like other opioids, can be diverted for non-medical use into illicit channels of distribution. Careful record-keeping of prescribing information, including quantity, frequency, and renewal requests, as required by state and federal law, is strongly advised.

Proper assessment of the patient, proper prescribing practices, periodic re-evaluation of therapy, and proper dispensing and storage are appropriate measures that help to limit abuse of opioid drugs.

Risks Specific to the Abuse of LAZANDA

LAZANDA is for intranasal transmucosal use only. Abuse of LAZANDA poses a risk of overdose and death. The risk is increased with concurrent abuse of LAZANDA with alcohol and other central nervous system depressants.

9.3 Dependence

Both tolerance and physical dependence can develop during chronic opioid therapy. Tolerance is the need for increasing doses of opioids to maintain a defined effect such as analgesia (in the absence of disease progression or other external factors). Tolerance may occur to both the desired and undesired effects of drugs, and may develop at different rates for different effects.

Physical dependence results in withdrawal symptoms after abrupt discontinuation or a significant dosage reduction of a drug. Withdrawal also may be precipitated through the administration of drugs with opioid antagonist activity (e.g., naloxone, nalmefene), mixed agonist/antagonist analgesics (e.g., pentazocine, butorphanol, nalbuphine), or partial agonists (e.g., buprenorphine). Physical dependence may not occur to a clinically significant degree until after several days to weeks of continued opioid usage.

Infants born to mothers physically dependent on opioids will also be physically dependent and may exhibit respiratory difficulties and withdrawal signs [see Use in Specific Populations (8.1)].

OVERDOSAGE

Clinical Presentation

Acute overdose with LAZANDA can be manifested by respiratory depression, somnolence progressing to stupor or coma, skeletal muscle flaccidity, cold and clammy skin, constricted pupils, and, in some cases, pulmonary edema, bradycardia, hypotension, partial or complete airway obstruction, atypical snoring, and death. Marked mydriasis rather than miosis may be seen with hypoxia in overdose situations [see Clinical Pharmacology (12.2)].

Treatment of Overdose

In case of overdose, priorities are: the reestablishment of a patent and protected airway and institution of assisted or controlled ventilation, if needed. Employ other supportive measures (including oxygen and vasopressors) in the management of circulatory shock and pulmonary edema as indicated. Cardiac arrest or arrhythmias will require advanced life-support techniques.

Opioid antagonists, such as naloxone, are specific antidotes to respiratory depression resulting from opioid overdose. For clinically significant respiratory or circulatory depression secondary to fentanyl overdose, administer an opioid antagonist.

Because the duration of opioid reversal is expected to be less than the duration of action of fentanyl in LAZANDA, carefully monitor the patient until spontaneous respiration is reliably re-established. If the response to an opioid antagonist is suboptimal or only brief in nature, administer additional antagonist as directed by the product’s prescribing information.

In an individual physically dependent on opioids, administration of the recommended usual dosage of the antagonist will precipitate an acute withdrawal syndrome. The severity of the withdrawal symptoms experienced will depend on the degree of physical dependence and the dose of the antagonist administered. If a decision is made to treat serious respiratory depression in the physically dependent patient, administration of the antagonist should be begun with care and by titration with smaller than usual doses of the antagonist.

DESCRIPTION

LAZANDA (fentanyl) nasal spray is a liquid formulation of fentanyl citrate, an opioid agonist, intended for intranasal transmucosal administration. The product consists of a practically clear to clear, colorless, aqueous solution of fentanyl citrate in a glass multidose container to which is attached a metered-dose nasal spray pump with a visual and audible spray counter. Each actuation is designed to deliver a spray of 100 mcL of solution containing 100 mcg, 300 mcg or 400 mcg fentanyl base, respectively. This enables doses of 100 mcg , 300 mcg or 400 mcg to be administered using a single spray into one nostril (1 spray) and 200 mcg, 600 mcg or 800 mcg to be administered using a single spray into both nostrils (2 sprays).

Active ingredient: Fentanyl citrate, USP is N-(l-phenethyl-4-piperidyl) propionanilide citrate (1:1). Fentanyl is a highly lipophilic compound (octanol-water partition coefficient at pH 7.4 is 816:1). Fentanyl citrate is sparingly soluble in water (1:40). The molecular weight of the free base and citrate salt are 336.5 and 528.6, respectively. The pKa is 8.4. The compound has the following structural formula:

LAZANDA is available in 3 strengths of nasal spray: 100 mcg fentanyl (yellow label), 300 mcg fentanyl (blue label) and 400 mcg fentanyl (violet label). The strength is expressed as the amount of fentanyl free base per spray, e.g., the 100 mcg strength provides 100 mcg of fentanyl free base per 100 mcL spray.

Inactive ingredients: mannitol, pectin, phenylethyl alcohol, propylparaben, sucrose, water. Sodium hydroxide and/or hydrochloric acid are added if required for pH adjustment.

CLINICAL PHARMACOLOGY SECTION

12.1 Mechanism of Action

Fentanyl is an opioid agonist whose principal therapeutic action is analgesia.

12.2 Pharmacodynamics

Effects on the Central Nervous System

Fentanyl produces respiratory depression by direct action on brain stem respiratory centers. The respiratory depression involves a reduction in the responsiveness of the brain stem respiratory centers to both increase in carbon dioxide tension and electrical stimulation.

Fentanyl causes miosis, even in total darkness. Pinpoint pupils are a sign of opioid overdose but are not pathognomonic (e.g., pontine lesions of hemorrhagic or ischemic origins may produce similar findings). Marked mydriasis rather than miosis may be seen due to hypoxia in overdose situations.

Effects on the Gastrointestinal Tract and Other Smooth Muscle

Fentanyl causes a reduction in motility associated with an increase in smooth muscle tone in the antrum of the stomach and duodenum. Digestion of food in the small intestine is delayed and propulsive contractions are decreased. Propulsive peristaltic waves in the colon are decreased, while tone may be increased to the point of spasm resulting in constipation. Other opioid-induced effects may include a reduction in biliary and pancreatic secretions, spasm of sphincter of Oddi, and transient elevations in serum amylase.

Effects on the Cardiovascular System

Fentanyl produces peripheral vasodilation which may result in orthostatic hypotension or syncope. Manifestations of histamine release and/or peripheral vasodilation may include pruritus, flushing, red eyes, sweating and/or orthostatic hypotension.

Effects on the Endocrine System

Opioids inhibit the secretion of adrenocorticotropic hormone (ACTH), cortisol, and luteinizing hormone (LH) in humans [see Adverse Reactions (6.2)]. They also stimulate prolactin, growth hormone (GH) secretion, and pancreatic secretion of insulin and glucagon.

Chronic use of opioids may influence the hypothalamic-pituitary-gonadal axis, leading to androgen deficiency that may manifest as low libido, impotence, erectile dysfunction, amenorrhea, or infertility. The causal role of opioids in the clinical syndrome of hypogonadism is unknown because the various medical, physical, lifestyle, and psychological stressors that may influence gonadal hormone levels have not been adequately controlled for in studies conducted to date [see Adverse Reactions (6.2)].

Effects on the Immune System

Opioids have been shown to have a variety of effects on components of the immune system in in vitro and animal models. The clinical significance of these findings is unknown. Overall, the effects of opioids appear to be modestly immunosuppressive.

Concentration–Efficacy Relationships

The analgesic effects of fentanyl are related to the blood level of the drug, if proper allowance is made for the delay into and out of the CNS (a process with a 3- to 5-minute half-life).

In general, the effective concentration and the concentration at which toxicity occurs increase with increasing tolerance with any and all opioids. The rate of development of tolerance varies widely among individuals.

The minimum effective analgesic concentration of fentanyl for any individual patient may increase over time due to an increase in pain, the development of a new pain syndrome and/or the development of analgesic tolerance [see Dosage and Administration (2.1, 2.5)].

Concentration–Adverse Reaction Relationships

There is a relationship between increasing fentanyl plasma concentration and increasing frequency of dose-related opioid adverse reactions such as nausea, vomiting, CNS effects, and respiratory depression. In opioid-tolerant patients, the situation may be altered by the development of tolerance to opioid-related adverse reactions [see Dosage and Administration (2.1, 2.2, 2.3)].

Respiratory System

All opioid mu-receptor agonists, including fentanyl, produce dose-dependent respiratory depression. The risk of respiratory depression is less in patients receiving chronic opioid therapy who develop tolerance to respiratory depression and other opioid effects. Peak respiratory depressive effects may be seen as early as 15 to 30 minutes from the start of transmucosal fentanyl citrate product administration and may persist for several hours.

Serious or fatal respiratory depression can occur even at recommended doses. Although not observed with oral or nasal transmucosal fentanyl products in clinical trials, fentanyl given rapidly by intravenous injection in large doses may interfere with respiration by causing rigidity in the muscles of respiration. [see Warnings and Precautions (5.1), Adverse Reactions (6), Overdosage (10)].

12.3 Pharmacokinetics

Absorption

In a study that compared the relative bioavailability of LAZANDA and an oral transmucosal fentanyl citrate product, the bioavailability of fentanyl from LAZANDA was approximately 20% higher. Fentanyl is absorbed from the nasal mucosa following intranasal administration of LAZANDA, with median Tmax values ranging from 15-21 min after administration of a single dose. Cmax and AUC values for fentanyl following administration of LAZANDA increase linearly over the 100- to 800-mcg dose range.

Mean plasma concentration versus time profiles are presented in Figure 1. Mean pharmacokinetic parameters are presented in Table 4.

Figure 1.

Mean Plasma Fentanyl Concentration (pg/mL) in Normal Subjects Receiving 100, 200, 400 and 800 mcg Lazanda or 200 mcg OTFC

Table 4. Pharmacokinetic Parameters in Normal Subjects Receiving 100, 200, 400, and 800 mcg of LAZANDA or 200 mcg OTFC

 | LAZANDA |  |  |  | OTFC
PHARMACOKINETIC PARAMETERS | 100 mcg | 200 mcg | 400 mcg | 800 mcg | 200 mcg
Tmax, hours; median (range) | 0.33; (0.08–1.50) | 0.25; (0.17–1.60) | 0.35; (0.25–0.75) | 0.34; (0.17–3.00) | 1.50; (0.50–8.00)
Cmax, pg/mL; Mean (%CV) | 351.5; (51.3) | 780.8; (48.4) | 1552.1; (26.2) | 2844.0; (56.0) | 317.4; (29.9)
AUCinf, pg.hour/mL; Mean (%CV) | 2460.5; (17.9) | 4359.9; (29.8) | 7513.4; (26.7) | 17272; (48.9) | 3735.0; (32.8)
t1/2, hour; Mean (%CV) | 21.9; (13.6) | 24.9; (51.3) | 15.0; (24.7) | 24.9; (92.5) | 18.6; (31.4)

A pharmacokinetic study evaluated the cerebrospinal fluid (CSF) concentrations of fentanyl administered via the intranasal (LAZANDA) route. As presented in Table 5, the maximum concentration of fentanyl in the CSF as delivered by LAZANDA was reached at 1.0 hour. Values for the Cmax and AUC0-6h of fentanyl are also presented in Table 5.

Table 5 Cerebrospinal Pharmacokinetic Parameters in Normal Subjects Receiving 200 mcg of LAZANDA

PHARMACOKINETICS PARAMETERS | LAZANDA (fentanyl nasal spray) 200 mcg
Tmax, hours; Median (range) | 1.01 (0.75–3.00)
Cmax, pg /mL; Mean (%CV) | 84.54; (55.7)
AUC0-6h, pg.hour/mL; Mean (%CV) | 300.25; (40.6)

In a pharmacokinetic study that evaluated multiple-dose pharmacokinetics of LAZANDA when two doses of LAZANDA are administered in the same nostril and are separated by a 1, 2 or 4 h time lapse, Cmax2 (Cmax after second administration) was greater than Cmax1 (Cmax after first administration), by 30% when LAZANDA was administered 1 h apart, by 25% when LAZANDA was administered 2 h apart and by 10% when LAZANDA was administered 4 h apart. Based on these results and based on Tmax range of LAZANDA observed across pharmacokinetic studies, and frequency of breakthrough pain episodes in a cancer population, a waiting period of 2 h between two consecutive doses of LAZANDA is recommended [see Dosage and Administration (2.3, 2.4)].

In a pharmacokinetic study to evaluate differences in LAZANDA absorption in individuals with induced allergic (seasonal) rhinitis using Ragweed, no clinically meaningful differences were observed in rate or extent of exposure to fentanyl, when compared to the Asymptomatic (Unchallenged) state, indicating that presence of allergic rhinitis does not affect LAZANDA absorption. This study also assessed differences in Lazanda absorption, if any, when co-administered with oxymetazoline, a nasal decongestant in subjects undergoing treatment for seasonal allergic rhinitis. The mean Cmax and AUCt values for Treated arm (Rhinitis treated with oxymetazoline) were about 32% and 10% lower , respectively compared to the Asymptomatic arm. In addition, mean Tmax of LAZANDA in the Treated arm was 0.75 h (range 0.08-3 h) as compared to 0.25 h (0.17-1 h) for the Asymptomatic arm. These results indicate that co-administration with oxymetazoline in rhinitis leads to lower peak plasma concentrations and delayed Tmax of LAZANDA [see Drug Interactions (7)].

Distribution

Fentanyl is highly lipophilic. The plasma protein binding of fentanyl is 80% to 85%. The main binding protein is alpha-1-acid glycoprotein, but both albumin and lipoproteins contribute to some extent. The mean volume of distribution at steady state (Vss) was 4 L/kg.

Elimination

The total plasma clearance of fentanyl following intravenous administration is approximately 42 L/h.

Metabolism

The metabolic pathways following intranasal administration of LAZANDA have not been characterized in clinical studies. The progressive decline of fentanyl plasma concentrations results from the uptake of fentanyl in the tissues and biotransformation in the liver. Fentanyl is metabolized in the liver and in the intestinal mucosa to norfentanyl by cytochrome P450 3A4 isoform. In animal studies, norfentanyl was not found to be pharmacologically active.

Excretion

The disposition of fentanyl following intranasal administration of LAZANDA has not been characterized in a mass balance study. Fentanyl is primarily (more than 90%) eliminated by biotransformation to N-dealkylated and hydroxylated inactive metabolites. Less than 7% of the administered dose is excreted unchanged in the urine, and only about 1% is excreted unchanged in the feces. The metabolites are mainly excreted in the urine, while fecal excretion is less important.

NONCLINICAL TOXICOLOY

Carcinogenesis

Long-term studies in animals to evaluate the carcinogenic potential of fentanyl have not been conducted.

Mutagenesis

Fentanyl citrate was not mutagenic in the in vitro Ames reverse mutation assay in S. typhimurium or E. coli, or the mouse lymphoma mutagenesis assay, and was not clastogenic in the in vivo mouse micronucleus assay.

Impairment of Fertility

Fentanyl has been shown to impair fertility in rats at doses of 30 mcg/kg subcutaneously. Conversion to human equivalent doses indicates this is within the range of the human recommended dosing for LAZANDA.

CLINICAL STUDIES

The efficacy of LAZANDA was evaluated in one clinical trial in opioid tolerant adult patients experiencing breakthrough cancer pain. Breakthrough cancer pain was defined as a transient flare of moderate-to-severe pain occurring in patients experiencing persistent cancer pain otherwise controlled with maintenance doses of opioid medications including at least 60 mg of oral morphine/day or an equianalgesic dose of another opioid (which could be fentanyl) for a week or longer. All patients were on stable doses of either long-acting oral opioids or transdermal fentanyl for their persistent cancer pain.

The clinical trial included an open-label titration phase where a dose was identified that provided adequate analgesia with tolerable side effects, within the range of 100 to 800 mcg. In the double-blind, placebo-controlled portion of the study, patients who were titrated to an adequate dose were randomized to a blinded sequence of 10 treatments with 7 being the identified dose of LAZANDA and 3 being placebo.

Of the patients who enrolled in the study, 73% achieved an adequate dose during the titration phase, 6% withdrew for lack of effective pain relief, and 5% withdrew due to adverse events.

The distribution of final titrated doses is shown in Table 5. The final titrated dose of LAZANDA for breakthrough pain was not predicted from the daily maintenance dose of opioid used to manage the persistent cancer pain and, therefore, the dose was determined by titration starting at 100 mcg.

Table 6. Dose of LAZANDA Following Initial Titration (ITT population)

LAZANDA Dose | (N=83) n (%)
100 mcg | 12 (14)
200 mcg | 7 (8)
400 mcg | 27 (33)
800 mcg | 37 (45)

The primary outcome measure, the mean sum of the pain intensity difference at 30 minutes (SPID30), was statistically significantly higher for LAZANDA than for placebo (see Figure 2).

Figure 2.

Pain Intensity Differences (PID) following LAZANDA or Placebo in Adult Patients with Breakthrough Cancer Pain

HOW SUPPLIED

LAZANDA is available as a 5.3 mL capacity clear glass bottle with an attached metered-dose nasal spray pump incorporating a visual and audible spray counter, and a protective dust cover. Each glass bottle, contains 8 sprays of 100 mcL available in three different concentrations: 100 mcg/100 mcL, 300 mcg/100 mcL or 400 mcg/100 mcL concentration solution. Each bottle contains a net fill weight of 1.57 grams and, after priming, delivers 8 sprays.

The pump will remain primed for up to 5 days after priming or use. If the product has not been used for 5 days, re-prime by spraying once. The nasal spray delivers 8 full sprays. There are 3 product strengths and each 100 mcL spray contains either 100 mcg, 300 mcg or 400 mcg of fentanyl. Each bottle is supplied in a child-resistant container.

Bottles in their child-resistant containers are supplied in cartons containing 1 bottle with instructions for use.

Each carton contains one carbon-lined pouch per bottle for disposal of priming sprays, unwanted doses and residual fentanyl solution.

Lazanda Dosage Strength; (fentanyl base) | Number of Bottles per Carton | NDC Number
100 mcg | 1 | 71500-110-01
300 mcg | 1 | 71500-130-01
400 mcg | 1 | 71500-140-01

Store at up to 25°C. Do not freeze.

Note: Carton and bottle label colors are a secondary aid in product identification. Confirm the printed dosage before dispensing.

Store LAZANDA securely and dispose of properly [see Patient Counseling Information (17)].

PATIENT COUNSELING

Storage and Disposal of Unused LAZANDA [see Instructions for Use]

- Because of the risks associated with accidental ingestion, misuse, and abuse, advise patients to store LAZANDA securely, out of sight and reach of children, and in a location not accessible by others, including visitors to the home [see Warnings and Precautions (5.2, 5.6), Drug Abuse and Dependence (9.2)]. Inform patients that leaving LAZANDA unsecured can pose a deadly risk to others in the home.
- Advise patients and caregivers to return the bottle to the child-resistant container after each use. Put the bottle in its child-resistant container and the pouch in the cardboard carton and store securely out of the reach of children and protect from light.
- Advise patients and caregivers that when medicines are no longer needed, they should be disposed of promptly. Inform patients that they can visit www.fda.gov/drugdisposal for a complete list of medicines recommended for disposal by flushing, as well as additional information on disposal of unused medicines.
- Instruct patients that, to dispose of LAZANDA properly, the remaining liquid in all bottles must be sprayed into the pouch provided in the pack for safe disposal as soon as possible. This includes any unwanted therapeutic sprays remaining in the bottle. After the counter has advanced to “8”, the patient should continue to push down on the finger grips a total of four times in order to expel any residual medicine from the bottle. After the 8 therapeutic sprays have been emitted, the patient will not hear a click and the counter will not advance beyond “8”; further sprays emitted will not be full sprays and should always be trapped in the pouch, not used therapeutically.
- Instruct the patient and caregiver to seal the pouch and to place both the empty bottle and the sealed pouch into the child-resistant storage container and discard in the trash. LAZANDA must be stored in the specially provided child-resistant container out of the reach of children until proper disposal is possible.
- Instruct the patient and caregiver to wash their hands with soap and water immediately after handling the pouch.
- If the pouch is lost, instruct the patient and caregiver to use a pouch from another LAZANDA pack to prime and dispose of unused medicine from the current bottle as well as from the next bottle. If they do not have an empty pouch available, the patient or caregiver can order one by calling 1-844-452-9263. They will receive the replacement pouch in the mail.

Advise the patient to read the FDA-approved patient labeling (Medication Guide).

Life-Threatening Respiratory Depression

Inform patients of the risk of life-threatening respiratory depression, including information that the risk is greatest when starting LAZANDA or when the dosage is increased, and that it can occur even at recommended dosages.

Educate patients and caregivers on how to recognize respiratory depression and emphasize the importance of calling 911 or getting emergency medical help right away in the event of a known or suspected overdose [see Warnings and Precautions (5.1)].

Patient Access to Naloxone for the Emergency Treatment of Opioid Overdose

Discuss with the patient and caregiver the availability of naloxone for the emergency treatment of opioid overdose, both when initiating and renewing treatment with LAZANDA. Inform patients and caregivers about the various ways to obtain naloxone as permitted by individual state naloxone dispensing and prescribing requirements or guidelines (e.g., by prescription, directly from a pharmacist, or as part of a community-based program) [see Dosage and Administration (2.2), Warnings and Precautions (5.1)].

Educate patients and caregivers on how to recognize the signs and symptoms of an overdose.

Explain to patients and caregivers that naloxone’s effects are temporary, and that they must call 911 or get emergency medical help right away in all cases of known or suspected opioid overdose, even if naloxone is administered [see Overdosage (10)].

If naloxone is prescribed, also advise patients and caregivers:

- How to treat with naloxone in the event of an opioid overdose
- To tell family and friends about their naloxone and to keep it in a place where family and friends can access it in an emergency
- To read the Patient Information (or other educational material) that will come with their naloxone. Emphasize the importance of doing this before an opioid emergency happens, so the patient and caregiver will know what to do.

Increased Risk of Overdose and Death in Children Due to Accidental Exposure

- Healthcare providers and dispensing pharmacists must specifically question patients or caregivers about the presence of children in the home (on a full time or visiting basis) and counsel them regarding the dangers to children from inadvertent exposure [see Warnings and Precautions (5.2)].
- Inform patients and their caregivers that accidental exposure, especially in children, may result in respiratory depression or death [see Warnings and Precautions (5.2)].
- Instruct patients and their caregivers that in the event that a LAZANDA unit is not completely consumed, it must be properly disposed as soon as possible [see Dosage and Administration (2.8), Patient Counseling Information; Disposal of Unused LAZANDA (17)].
- Instruct patients and caregivers to keep both used and unused LAZANDA out of the reach of children [see Warnings and Precautions (5.2)].

Interactions with Benzodiazepines and Other CNS Depressants

Inform patients that potentially fatal additive effects may occur if LAZANDA is used with benzodiazepines or other CNS depressants, including alcohol, and not to use these concomitantly unless supervised by a health care provider [see Warnings and Precautions (5.4), Drug Interactions (7)]

Addiction, Abuse, and Misuse

Inform patients that the use of LAZANDA, even when taken as recommended, can result in addiction, abuse, and misuse, which can lead to overdose and death [see Warnings and Precautions (5.6)]. Instruct patients not to share LAZANDA with others and to take steps to protect LAZANDA from theft or misuse.

Transmucosal Immediate-Release Fentanyl (TIRF) REMS

LAZANDA is available only through a restricted program called the Transmucosal Immediate Release Fentanyl (TIRF) REMS [see Warnings and Precautions (5.7)]. Inform the patient of the following notable requirements:

- Outpatients must be enrolled in the REMS program
- Patients must be opioid-tolerant to receive LAZANDA

LAZANDA is available only from certified pharmacies participating in this program. Therefore, provide patients with the telephone number and website for information on how to obtain the product.

Pharmacies, outpatients, and healthcare professionals who prescribe to outpatients are required to enroll in the program. Inpatient pharmacies must develop policies and procedures to verify opioid tolerance in inpatients who require LAZANDA while hospitalized [see Warnings and Precautions (5.7)].

Serotonin Syndrome

Inform patients that opioids could cause a rare but potentially life-threatening condition resulting from concomitant administration of serotonergic drugs. Warn patients of the symptoms of serotonin syndrome and to seek medical attention right away if symptoms develop. Instruct patients to inform their physicians if they are taking, or plan to take serotonergic medications. [see Warnings and Precautions (5.10), Drug Interactions (7)].

MAOI Interaction

Inform patients to avoid taking LAZANDA while using any drugs that inhibit monoamine oxidase. Patients should not start MAOIs while taking LAZANDA [see Warnings and Precautions (5.10); Drug Interactions (7)].

Adrenal Insufficiency

Inform patients that opioids could cause adrenal insufficiency, a potentially life-threatening condition. Adrenal insufficiency may present with non-specific symptoms and signs such as nausea, vomiting, anorexia, fatigue, weakness, dizziness, and low blood pressure. Advise patients to seek medical attention if they experience a constellation of these symptoms [see Warnings and Precautions (5.11)].

Important Administration Instructions [see Dosage and Administration (2)]

- Instruct patients not to take LAZANDA for acute pain, postoperative pain, pain from injuries, headache, migraine, or any other short-term pain, even if they have taken other opioid analgesics for these conditions.
- Instruct patients on the meaning of opioid tolerance and LAZANDA is only to be used as a supplemental pain medication for patients with pain requiring regular opioids, who have developed tolerance to the opioid medication and who need additional opioid treatment of breakthrough pain episodes.
- Instruct patients that if they are not taking an opioid medication on a regular around-the-clock basis, they should not take LAZANDA.
- Advise patients that LAZANDA contains fentanyl, which is a pain medication similar to hydromorphone, methadone, morphine, oxycodone, oxymorphone, hydrocodone, and tapentadol.
- Instruct patients that they MUST wait at least 2 hours before treating another episode of breakthrough pain with LAZANDA.
- Instruct patients to talk to their doctor if breakthrough pain is not alleviated or worsens after taking LAZANDA.
- Instruct patients to use LAZANDA exactly as prescribed by their doctor and not to take LAZANDA more often than prescribed.
- Instruct patients NOT to share LAZANDA and that sharing LAZANDA with anyone else could result in the other individual’s death due to overdose.
- Instruct patients and their caregivers that the amount of fentanyl contained in a bottle can be fatal to a child. Patients and their caregivers must be instructed to keep LAZANDA in its child-resistant container at all times and to store it and the pouch securely and out of the reach of children.

Hypotension

Inform patients that LAZANDA may cause orthostatic hypotension and syncope. Instruct patients how to recognize symptoms of low blood pressure and how to reduce the risk of serious consequences should hypotension occur (e.g., sit or lie down, carefully rise from a sitting or lying position) [see Warnings and Precautions (5.12)].

Anaphylaxis

Inform patients that anaphylaxis have been reported with ingredients contained in LAZANDA. Advise patients how to recognize such a reaction and when to seek medical attention [see Contraindications (4), Adverse Reactions (6.2)].

Pregnancy

Neonatal Opioid Withdrawal Syndrome

Inform patients that prolonged use of LAZANDA during pregnancy can result in neonatal opioid withdrawal syndrome, which may be life-threatening if not recognized and treated [see Warnings and Precautions (5.8), Use in Specific Populations (8.1)].

Embryo-Fetal Toxicity

Inform female patients of reproductive potential that LAZANDA can cause fetal harm and to inform their healthcare provider of a known or suspected pregnancy [see Use in Specific Populations (8.1)].

Lactation

Advise nursing mothers to monitor infants for increased sleepiness (more than usual), breathing difficulties, or limpness. Instruct nursing mothers to seek immediate medical care if they notice these signs [see Use in Specific Populations (8.2)].

Infertility

Inform patients that chronic use of opioids may cause reduced fertility. It is not known whether these effects on fertility are reversible [see Use in Specific Populations (8.3)].

Driving or Operating Heavy Machinery

Inform patients that LAZANDA may impair the ability to perform potentially hazardous activities such as driving a car or operating heavy machinery. Advise patients not to perform such tasks until they know how they will react to the medication [see Warnings and Precautions (5.16)].

Constipation

Advise patients of the potential for severe constipation, including management instructions and when to seek medical attention [see Adverse Reactions (6.1)].

Manufactured for: West Therapeutic Development, LLC

Northbrook, IL 60062

For information about this product call:

1-844-452-9263

141011

Lazanda is a registered trademark of West Therapeutic Development, LLC

© 2020 West Therapeutic Development, LLC

March 2021

LAZ-005-C.5

PRINCIPAL DISPLAY PANEL - 100 MCG 1-BOTTLE CARTON

NDC 71500-110-01

100 mcg per spray

Lazanda®
fentanyl nasal spray CII

For nasal administration only

Dispense the enclosed
Medication Guide to each patient

1 bottle, containing 8 sprays, and 1 disposal pouch

WARNING:
Keep out of the reach of children

PATIENTS MUST BE TOLERANT TO
AROUND-THE-CLOCK OPIOID THERAPY

DO NOT SUBSTITUTE LAZANDA
FOR OTHER FENTANYL PRODUCTS

Lazanda can be harmful or fatal if
given to someone for whom it was
not prescribed

Store the bottle in the child resistant
container at all times, even when finished.

PRINCIPAL DISPLAY PANEL - 300 MCG 1-BOTTLE CARTON

NDC 71500-130-01

300 mcg per spray

Lazanda®
fentanyl nasal spray CII

For nasal administration only

Dispense the enclosed
Medication Guide to each patient

1 bottle, containing 8 sprays, and 1 disposal pouch

WARNING:
Keep out of the reach of children

PATIENTS MUST BE TOLERANT TO
AROUND-THE-CLOCK OPIOID THERAPY

DO NOT SUBSTITUTE LAZANDA
FOR OTHER FENTANYL PRODUCTS

Lazanda can be harmful or fatal if
given to someone for whom it was
not prescribed

Store the bottle in the child resistant
container at all times, even when finished.

PRINCIPAL DISPLAY PANEL - 400 MCG 1-BOTTLE CARTON

NDC 71500-140-01

400 mcg per spray

Lazanda®
fentanyl nasal spray CII

For nasal administration only

Dispense the enclosed
Medication Guide to each patient

1 bottle, containing 8 sprays, and 1 disposal pouch

WARNING:
Keep out of the reach of children

PATIENTS MUST BE TOLERANT TO
AROUND-THE-CLOCK OPIOID THERAPY

DO NOT SUBSTITUTE LAZANDA
FOR OTHER FENTANYL PRODUCTS

Lazanda can be harmful or fatal if
given to someone for whom it was
not prescribed

Store the bottle in the child resistant
container at all times, even when finished.